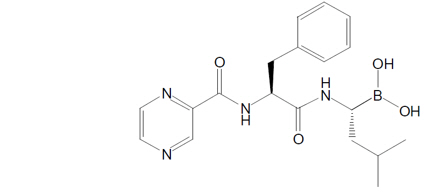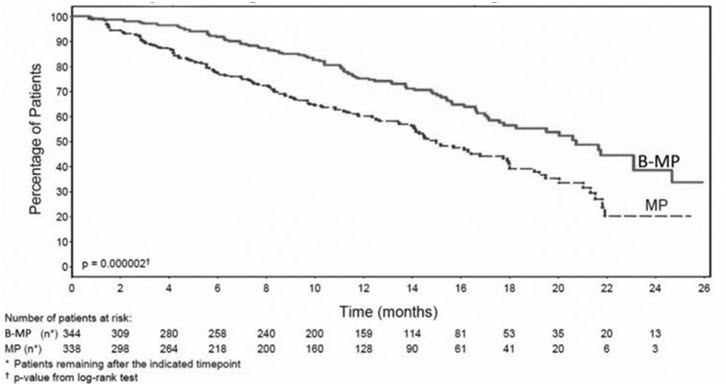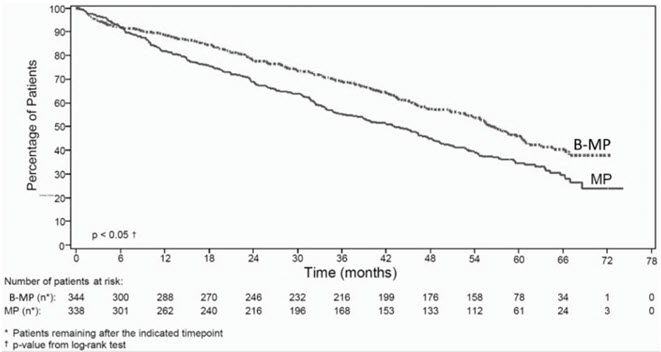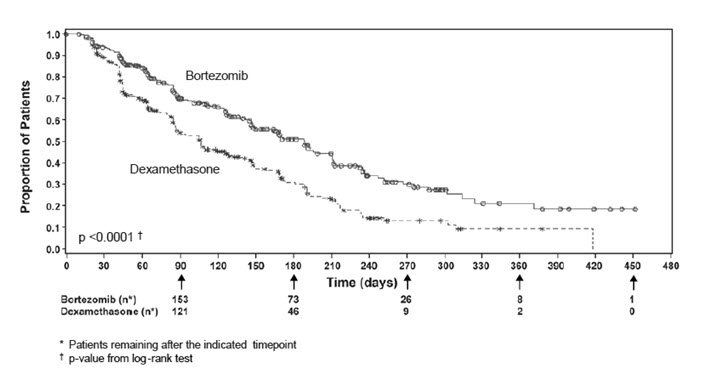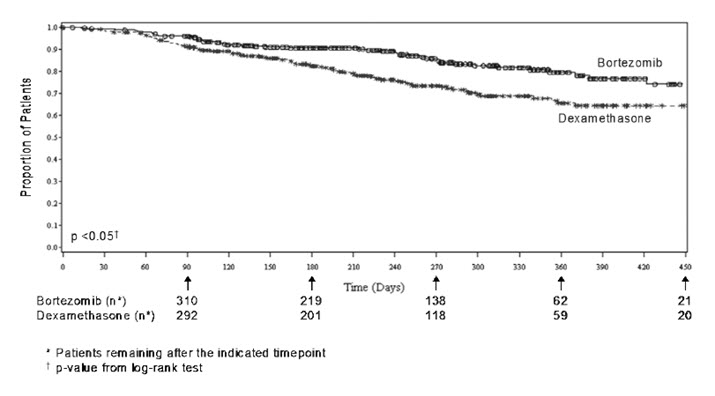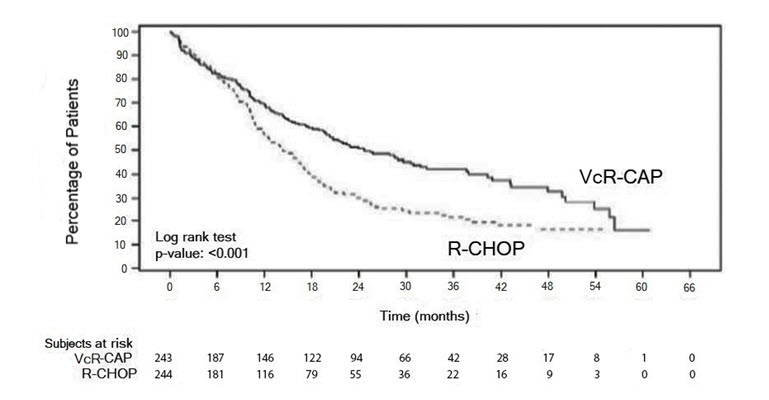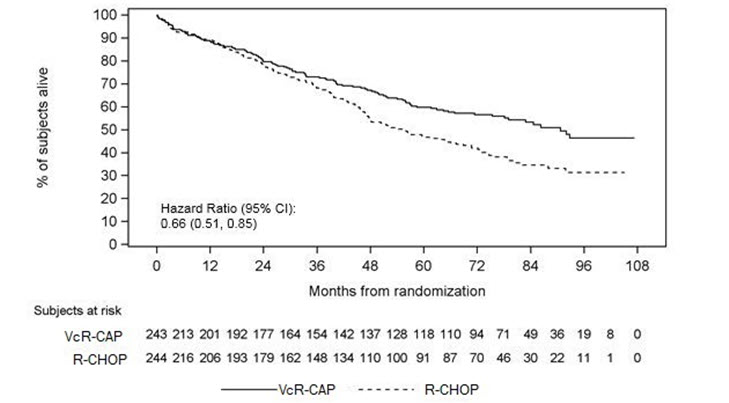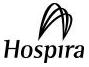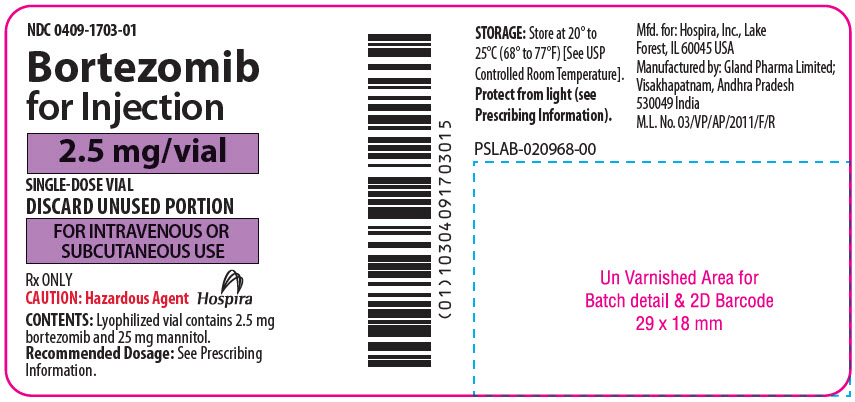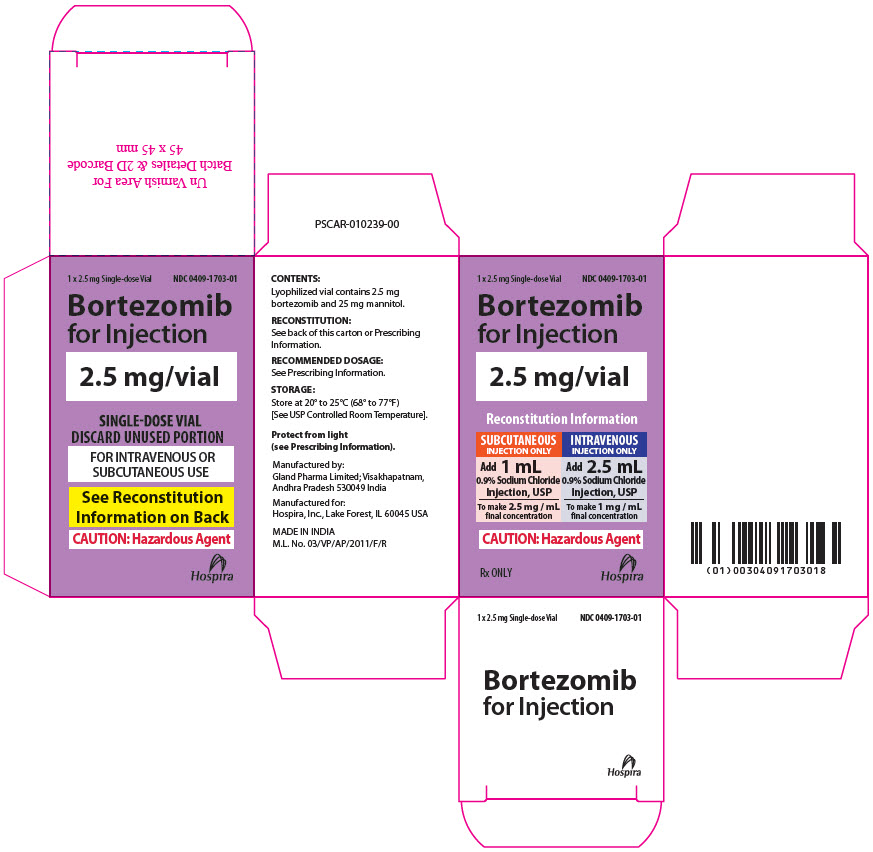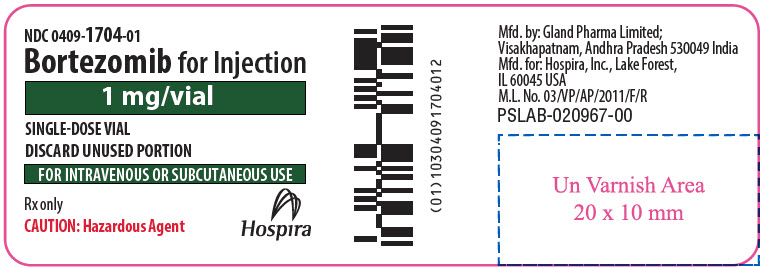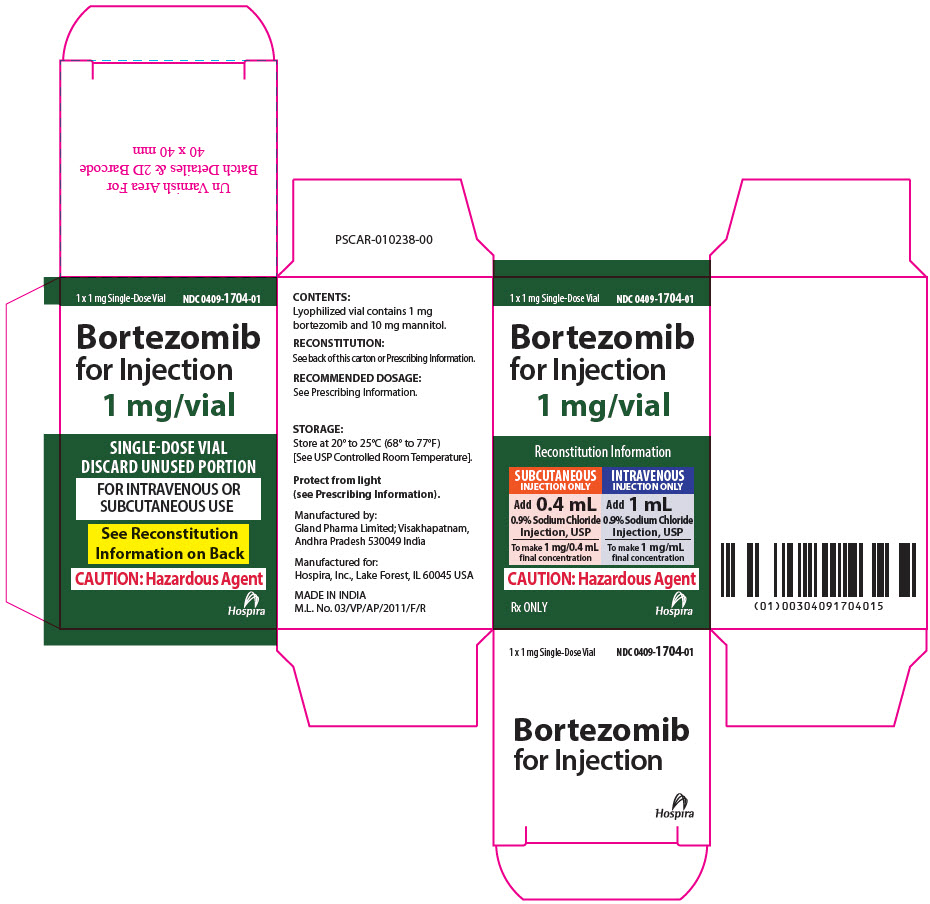 DRUG LABEL: BORTEZOMIB
NDC: 0409-1703 | Form: INJECTION, POWDER, LYOPHILIZED, FOR SOLUTION
Manufacturer: Hospira, Inc.
Category: prescription | Type: HUMAN PRESCRIPTION DRUG LABEL
Date: 20230227

ACTIVE INGREDIENTS: BORTEZOMIB 2.5 mg/1 1
INACTIVE INGREDIENTS: MANNITOL 25 mg/1 1

HIGHLIGHTS OF PRESCRIBING INFORMATION

These highlights do not include all the information needed to use BORTEZOMIB FOR INJECTION safely and effectively. See full prescribing information for BORTEZOMIB FOR INJECTION.
BORTEZOMIB for injection, for subcutaneous or intravenous use
Initial U.S. Approval: 2003

RECENT MAJOR CHANGES

Indications and Usage, Mantle Cell Lymphoma (1.2), Removed phrase “who have received at least 1 prior therapy” | 12/2022
Dosage and Administration (2.4, 2.5, 2.6, 2.7, 2.8, 2.9, 2.10) | 12/2022
Warnings and Precautions, Thrombocytopenia/Neutropenia (5.7) | 12/2022

1 INDICATIONS AND USAGE

Bortezomib for Injection is a proteasome inhibitor indicated for:

- Treatment of adult patients with multiple myeloma. (1.1)
- Treatment of adult patients with mantle cell lymphoma. (1.2)

2 DOSAGE AND ADMINISTRATION

- For subcutaneous or intravenous use only. Each route of administration has a different reconstituted concentration; Exercise caution when calculating the volume to be administered. (2.1, 2.10)
- The recommended starting dose of Bortezomib for Injection is 1.3 mg/m^2 administered either as a 3 to 5 second bolus intravenous injection or subcutaneous injection. (2.2, 2.4, 2.6)
- Retreatment for multiple myeloma: May retreat starting at the last tolerated dose. (2.6)
- Hepatic Impairment: Use a lower starting dose for patients with moderate or severe hepatic impairment. (2.8)
- Dose must be individualized to prevent overdose. (2.10)

3 DOSAGE FORMS AND STRENGTHS

For injection: 1 mg or 2.5 mg of bortezomib as a lyophilized powder in a single-dose vial for reconstitution and withdrawal of the appropriate individual patient dose. (3)

4 CONTRAINDICATIONS

- Patients with hypersensitivity (not including local reactions) to bortezomib, boron, or mannitol, including anaphylactic reactions. (4)
- Contraindicated for intrathecal administration. (4)

5 WARNINGS AND PRECAUTIONS

- Peripheral Neuropathy: Manage with dose modification or discontinuation. (2.7) Patients with pre-existing severe neuropathy should be treated with Bortezomib for Injection only after careful risk-benefit assessment. (2.7, 5.1)
- Hypotension: Use caution when treating patients taking antihypertensives, with a history of syncope, or with dehydration. (5.2)
- Cardiac Toxicity: Worsening of and development of cardiac failure has occurred. Closely monitor patients with existing heart disease or risk factors for heart disease. (5.3)
- Pulmonary Toxicity: Acute respiratory syndromes have occurred. Monitor closely for new or worsening symptoms and consider interrupting Bortezomib for Injection therapy. (5.4)
- Posterior Reversible Encephalopathy Syndrome: Consider MRI imaging for onset of visual or neurological symptoms; discontinue Bortezomib for Injection if suspected. (5.5)
- Gastrointestinal Toxicity: Nausea, diarrhea, constipation, and vomiting may require use of antiemetic and antidiarrheal medications or fluid replacement. (5.6)
- Thrombocytopenia/Neutropenia: Monitor complete blood counts regularly throughout treatment. (5.7)
- Tumor Lysis Syndrome: Closely monitor patients with high tumor burden. (5.8)
- Hepatic Toxicity: Monitor hepatic enzymes during treatment. Interrupt Bortezomib for Injection therapy to assess reversibility. (5.9)
- Thrombotic Microangiopathy: Monitor for signs and symptoms. Discontinue Bortezomib for Injection if suspected. (5.10)
- Embryo-Fetal Toxicity: Bortezomib for Injection can cause fetal harm. Advise females of reproductive potential and males with female partners of reproductive potential of the potential risk to a fetus and to use effective contraception. (5.11)

6 ADVERSE REACTIONS

Most commonly reported adverse reactions (incidence ≥20%) in clinical studies include nausea, diarrhea, thrombocytopenia, neutropenia, peripheral neuropathy, fatigue, neuralgia, anemia, leukopenia, constipation, vomiting, lymphopenia, rash, pyrexia, and anorexia. (6.1)

To report SUSPECTED ADVERSE REACTIONS, contact Pfizer Inc., at 1-800-438-1985 or FDA at 1-800-FDA-1088 or www.fda.gov/medwatch.

7 DRUG INTERACTIONS

- Strong CYP3A4 Inhibitors: Closely monitor patients with concomitant use. (7.1)
- Strong CYP3A4 Inducers: Avoid concomitant use. (7.1)

8 USE IN SPECIFIC POPULATIONS

Patients with diabetes may require close monitoring of blood glucose and adjustment of antidiabetic medication. (8.8)

FULL PRESCRIBING INFORMATION

1 INDICATIONS AND USAGE

1.1 Multiple Myeloma

Bortezomib for Injection is indicated for the treatment of adult patients with multiple myeloma.

1.2 Mantle Cell Lymphoma

Bortezomib for Injection is indicated for the treatment of adult patients with mantle cell lymphoma.

2 DOSAGE AND ADMINISTRATION

2.1 Important Dosing Guidelines

Bortezomib for Injection is for intravenous or subcutaneous use only. Do not administer Bortezomib for Injection by any other route.

Because each route of administration has a different reconstituted concentration, use caution when calculating the volume to be administered.

The recommended starting dose of Bortezomib for Injection is 1.3 mg/m^2. Bortezomib for Injection is administered intravenously at a concentration of 1 mg/mL, or subcutaneously at a concentration of 2.5 mg/mL [see Dosage and Administration (2.10)].

Bortezomib for Injection retreatment may be considered for patients with multiple myeloma who had previously responded to treatment with Bortezomib for Injection and who have relapsed at least six months after completing prior Bortezomib for Injection treatment. Treatment may be started at the last tolerated dose [see Dosage and Administration (2.6)].

When administered intravenously, administer Bortezomib for Injection as a 3 to 5 second bolus intravenous injection.

2.2 Dosage in Previously Untreated Multiple Myeloma

Bortezomib for Injection is administered in combination with oral melphalan and oral prednisone for 9, six-week treatment cycles as shown in Table 1. In Cycles 1 to 4, Bortezomib for Injection is administered twice weekly (Days 1, 4, 8, 11, 22, 25, 29 and 32). In Cycles 5 to 9, Bortezomib for Injection is administered once weekly (Days 1, 8, 22 and 29). At least 72 hours should elapse between consecutive doses of Bortezomib for Injection.

Table 1: Dosage Regimen for Patients with Previously Untreated Multiple Myeloma
Twice Weekly Bortezomib for Injection (Cycles 1 to 4)
Week | 1 |  |  |  | 2 |  | 3 | 4 |  | 5 |  | 6
Bortezomib for Injection (1.3 mg/m^2) | Day 1 | -- | -- | Day 4 | Day 8 | Day 11 | rest period | Day 22 | Day 25 | Day 29 | Day 32 | rest period
Melphalan (9 mg/m^2) Prednisone (60 mg/m^2) | Day 1 | Day 2 | Day 3 | Day 4 | -- | -- | rest period | -- | -- | -- | -- | rest period
Once Weekly Bortezomib for Injection (Cycles 5 to 9 when used in combination with Melphalan and Prednisone)
Week | 1 |  |  |  | 2 |  | 3 | 4 |  | 5 |  | 6
Bortezomib for Injection (1.3 mg/m^2) | Day 1 | -- | -- |  | Day 8 |  | rest period | Day 22 |  | Day 29 |  | rest period
Melphalan (9 mg/m^2) Prednisone (60 mg/m^2) | Day 1 | Day 2 | Day 3 | Day 4 | -- | -- | rest period | -- | -- | -- | -- | rest period

2.3 Dose Modification Guidelines for Bortezomib for Injection When Given in Combination with Melphalan and Prednisone

Prior to initiating any cycle of therapy with Bortezomib for Injection in combination with melphalan and prednisone:

- Platelet count should be at least 70 × 10^9/L and the absolute neutrophil count (ANC) should be at least 1 × 10^9/L
- Non-hematological toxicities should have resolved to Grade 1 or baseline

Table 2: Dose Modifications During Cycles of Combination Bortezomib for Injection, Melphalan and Prednisone Therapy
Toxicity | Dose Modification or Delay
Hematological toxicity during a cycle: If prolonged Grade 4 neutropenia or thrombocytopenia, or thrombocytopenia with bleeding is observed in the previous cycle | Consider reduction of the melphalan dose by 25% in the next cycle
If platelet count is not above 30 × 10^9/L or ANC is not above 0.75 × 10^9/L on a Bortezomib for Injection dosing day (other than Day 1) | Withhold Bortezomib for Injection dose
If several Bortezomib for Injection doses in consecutive cycles are withheld due to toxicity | Reduce Bortezomib for Injection dose by one dose level (from 1.3 mg/m^2 to 1 mg/m^2, or from 1 mg/m^2 to 0.7 mg/m^2)
Grade 3 or higher non-hematological toxicities | Withhold Bortezomib for Injection therapy until symptoms of toxicity have resolved to Grade 1 or baseline. Then, Bortezomib for Injection may be reinitiated with one dose level reduction (from 1.3 mg/m^2 to 1 mg/m^2, or from 1 mg/m^2 to 0.7 mg/m^2). For Bortezomib for Injection-related neuropathic pain and/or peripheral neuropathy, hold or modify Bortezomib for Injection as outlined in Table 5.

For information concerning melphalan and prednisone, see manufacturer's prescribing information.

Dose modifications guidelines for peripheral neuropathy are provided [see Dosage and Administration (2.7)].

2.4 Dosage in Previously Untreated Mantle Cell Lymphoma

Bortezomib (1.3 mg/m^2) is administered intravenously in combination with intravenous rituximab, cyclophosphamide, doxorubicin and oral prednisone (VcR-CAP) for 6, three week treatment cycles as shown in Table 3. Bortezomib is administered first followed by rituximab. Bortezomib is administered twice weekly for two weeks (Days 1, 4, 8, and 11) followed by a ten day rest period on Days 12 to 21. For patients with a response first documented at Cycle 6, two additional VcR-CAP cycles are recommended. At least 72 hours should elapse between consecutive doses of bortezomib.

Table 3: Dosage Regimen for Patients with Previously Untreated Mantle Cell Lymphoma Twice Weekly Bortezomib (6, Three Week Cycles) [Dosing may continue for two more cycles (for a total of eight cycles) if response is first seen at Cycle 6.]
Week | 1 |  |  |  |  | 2 |  | 3
Bortezomib (1.3 mg/m^2) | Day 1 | -- | -- | Day 4 | -- | Day 8 | Day 11 | rest period
Rituximab (375 mg/m^2) Cyclophosphamide (750 mg/m^2) Doxorubicin (50 mg/m^2) | Day 1 | -- | -- |  |  | -- | -- | rest period
Prednisone (100 mg/m^2) | Day 1 | Day 2 | Day 3 | Day 4 | Day 5 | -- | -- | rest period

2.5 Dose Modification Guidelines for Bortezomib When Given in Combination with Rituximab, Cyclophosphamide, Doxorubicin and Prednisone

Prior to the first day of each cycle (other than Cycle 1):

- Platelet count should be at least 100 × 10^9/L and absolute neutrophil count (ANC) should be at least 1.5 × 10^9/L
- Hemoglobin should be at least 8 g/dL (at least 4.96 mmol/L)
- Nonhematologic toxicity should have recovered to Grade 1 or baseline

Interrupt bortezomib treatment at the onset of any Grade 3 hematologic or nonhematological toxicities, excluding neuropathy [see Table 5, Warnings and Precautions (5)]. For dose adjustments, see Table 4 below.

Table 4: Dose Modifications on Days 4, 8, and 11 During Cycles of Combination Bortezomib, Rituximab, Cyclophosphamide, Doxorubicin and Prednisone Therapy
Toxicity | Dose Modification or Delay
Hematological Toxicity
Grade 3 or higher neutropenia, or a platelet count not at or above 25 × 10^9/L | Withhold bortezomib therapy for up to 2 weeks until the patient has an ANC at or above 0.75 × 10^9/L and a platelet count at or above 25 × 10^9/L.; - If, after bortezomib has been withheld, the toxicity does not resolve, discontinue bortezomib. - If toxicity resolves such that the patient has an ANC at or above 0.75 × 10^9/L and a platelet count at or above 25 × 10^9/L, bortezomib dose should be reduced by 1 dose level (from 1.3 mg/m^2 to 1 mg/m^2, or from 1 mg/m^2 to 0.7 mg/m^2).
Grade 3 or higher nonhematological toxicities | Withhold bortezomib therapy until symptoms of the toxicity have resolved to Grade 2 or better. Then, bortezomib may be reinitiated with one dose level reduction (from 1.3 mg/m^2 to 1 mg/m^2, or from 1 mg/m^2 to 0.7 mg/m^2). For bortezomib-related neuropathic pain and/or peripheral neuropathy, hold or modify bortezomib as outlined in Table 5.

For information concerning rituximab, cyclophosphamide, doxorubicin and prednisone, see manufacturer's prescribing information.

2.6 Dosage and Dose Modifications for Relapsed Multiple Myeloma and Relapsed Mantle Cell Lymphoma

Bortezomib for Injection (1.3 mg/m^2/dose) is administered twice weekly for two weeks (Days 1, 4, 8, and 11) followed by a ten day rest period (Days 12 to 21). For extended therapy of more than eight cycles, Bortezomib for Injection may be administered on the standard schedule or, for relapsed multiple myeloma, on a maintenance schedule of once weekly for four weeks (Days 1, 8, 15, and 22) followed by a 13 day rest period (Days 23 to 35) [see Clinical Studies (14)]. At least 72 hours should elapse between consecutive doses of Bortezomib for Injection.

Patients with multiple myeloma who have previously responded to treatment with Bortezomib for Injection (either alone or in combination) and who have relapsed at least six months after their prior Bortezomib for Injection therapy may be started on Bortezomib for Injection at the last tolerated dose. Retreated patients are administered Bortezomib for Injection twice weekly (Days 1, 4, 8, and 11) every three weeks for a maximum of eight cycles. At least 72 hours should elapse between consecutive doses of Bortezomib for Injection. Bortezomib for Injection may be administered either as a single agent or in combination with dexamethasone [see Clinical Studies (14.1)].

Bortezomib for Injection therapy should be withheld at the onset of any Grade 3 non-hematological or Grade 4 hematological toxicities excluding neuropathy as discussed below [see Warnings and Precautions (5)]. Once the symptoms of the toxicity have resolved, Bortezomib for Injection therapy may be reinitiated at a 25% reduced dose (1.3 mg/m^2/dose reduced to 1 mg/m^2/dose; 1 mg/m^2/dose reduced to 0.7 mg/m^2/dose).

For dose modifications guidelines for peripheral neuropathy, see section 2.7.

2.7 Dose Modifications for Peripheral Neuropathy

Starting Bortezomib for Injection subcutaneously may be considered for patients with pre-existing or at high risk of peripheral neuropathy. Patients with pre-existing severe neuropathy should be treated with Bortezomib for Injection only after careful risk-benefit assessment.

Patients experiencing new or worsening peripheral neuropathy during Bortezomib for Injection therapy may require a decrease in the dose and/or a less dose-intense schedule.

For dose or schedule modification guidelines for patients who experience Bortezomib for Injection-related neuropathic pain and/or peripheral neuropathy, see Table 5.

Table 5: Recommended Dose Modification for Bortezomib for Injection related Neuropathic Pain and/or Peripheral Sensory or Motor Neuropathy
Severity of Peripheral Neuropathy Signs and Symptoms [Grading based on NCI Common Terminology Criteria CTCAE v4.0] | Modification of Dose and Regimen
Grade 1 (asymptomatic; loss of deep tendon reflexes or paresthesia) without pain or loss of function | No action
Grade 1 with pain or Grade 2 (moderate symptoms; limiting instrumental Activities of Daily Living (ADL) [Instrumental ADL: refers to preparing meals, shopping for groceries or clothes, using telephone, managing money, etc.;]) | Reduce Bortezomib for Injection to 1 mg/m^2
Grade 2 with pain or Grade 3 (severe symptoms; limiting self care ADL [Self care ADL: refers to bathing, dressing and undressing, feeding self, using the toilet, taking medications, and not bedridden]) | Withhold Bortezomib for Injection therapy until toxicity resolves. When toxicity resolves reinitiate with a reduced dose of Bortezomib for Injection at 0.7 mg/m^2 once per week.
Grade 4 (life-threatening consequences; urgent intervention indicated) | Discontinue Bortezomib for Injection

2.8 Dosage in Patients with Hepatic Impairment

Do not adjust the starting dose for patients with mild hepatic impairment.

Start patients with moderate or severe hepatic impairment at a reduced dose of 0.7 mg/m^2 per injection during the first cycle, and consider subsequent dose escalation to 1 mg/m^2 or further dose reduction to 0.5 mg/m^2 based on patient tolerance (see Table 6) [see Use in Specific Populations (8.7), Clinical Pharmacology (12.3)].

Table 6: Recommended Starting Dose Modification for Bortezomib for Injection in Patients with Hepatic Impairment
 | Bilirubin Level | SGOT (AST) Levels | Modification of Starting Dose
Mild | Less than or equal to 1× ULN | More than ULN | None
Mild | More than 1× to 1.5× ULN | Any | None
Moderate | More than 1.5× to 3× ULN | Any | Reduce dose to 0.7 mg/m^2 in the first cycle. Consider dose escalation to 1 mg/m^2 or further dose reduction to 0.5 mg/m^2 in subsequent cycles based on patient tolerability.
Severe | More than 3× ULN | Any | Reduce dose to 0.7 mg/m^2 in the first cycle. Consider dose escalation to 1 mg/m^2 or further dose reduction to 0.5 mg/m^2 in subsequent cycles based on patient tolerability.
Abbreviations: SGOT = serum glutamic oxaloacetic transaminase; AST = aspartate aminotransferase; ULN = upper limit of the normal range.

2.9 Administration Precautions

The drug quantity contained in one vial (1 mg or 2.5 mg) may exceed the usual dose required. Use caution when calculating the dose to prevent overdose [see Dosage and Administration (2.10)].

When administered subcutaneously, rotate sites for each injection (thigh or abdomen). Give new injections at least one inch from an old site and never into areas where the site is tender, bruised, erythematous, or indurated.

If local injection site reactions occur following Bortezomib for Injection administration subcutaneously, a less concentrated Bortezomib for Injection solution (1 mg/mL instead of 2.5 mg/mL) may be administered subcutaneously [see Dosage and Administration (2.10)]. Alternatively, consider use of the intravenous route of administration [see Dosage and Administration (2.10)].

Bortezomib for Injection is a hazardous drug. Follow applicable special handling and disposal procedures. 1

2.10 Reconstitution/Preparation for Intravenous and Subcutaneous Administration

Use proper aseptic technique. Reconstitute only with 0.9% Sodium Chloride Injection, USP. The reconstituted product should be a clear and colorless solution.

Different volumes of 0.9% Sodium Chloride Injection, USP are used to reconstitute the product for the different routes of administration. The reconstituted concentration of bortezomib for subcutaneous administration (2.5 mg/mL) is greater than the reconstituted concentration of bortezomib for intravenous administration (1 mg/mL). Because each route of administration has a different reconstituted concentration, use caution when calculating the volume to be administered [see Dosage and Administration (2.9)].

For each 1 mg or 2.5 mg single-dose vial of bortezomib, reconstitute with the following volume of 0.9% Sodium Chloride Injection, USP based on route of administration (Table 7):

Table 7: Reconstitution Volumes and Final Concentration for Intravenous and Subcutaneous Administration
Route of Administration | Bortezomib (mg/vial) | Diluent (0.9% Sodium Chloride Injection, USP) | Final Bortezomib Concentration
Intravenous | 1 mg | 1 mL | 1 mg/mL
Subcutaneous | 1 mg | 0.4 mL | 2.5 mg/mL [Actual vial content results in a final concentration of 1 mg/0.4 mL]
Intravenous | 2.5 mg | 2.5 mL | 1 mg/mL
Subcutaneous | 2.5 mg | 1 mL | 2.5 mg/mL

Dose must be individualized to prevent overdosage. After determining patient body surface area (BSA) in square meters, use the following equations to calculate the total volume (mL) of reconstituted Bortezomib for Injection to be administered:

- Intravenous Administration [1 mg/mL concentration]

 | Bortezomib for Injection dose (mg/m^2) × patient BSA (m^2) |  | = Total Bortezomib for Injection volume (mL) to be administered
 | 1 mg/mL

- Subcutaneous Administration [2.5 mg/mL concentration]

 | Bortezomib for Injection dose (mg/m^2) × patient BSA (m^2) |  | = Total Bortezomib for Injection volume (mL) to be administered
 | 2.5 mg/mL

Stickers that indicate the route of administration are provided with each Bortezomib for Injection vial. These stickers should be placed directly on the syringe of Bortezomib for Injection once Bortezomib for Injection is prepared to help alert practitioners of the correct route of administration for Bortezomib for Injection.

Parenteral drug products should be inspected visually for particulate matter and discoloration prior to administration whenever solution and container permit. If any discoloration or particulate matter is observed, the reconstituted product should not be used.

Stability

Unopened vials of Bortezomib for Injection are stable until the date indicated on the package when stored in the original package protected from light.

Bortezomib for Injection contains no antimicrobial preservative. Administer reconstituted Bortezomib for Injection within eight hours of preparation. When reconstituted as directed, Bortezomib for Injection may be stored at 25°C (77°F). The reconstituted material may be stored in the original vial and/or the syringe prior to administration. The product may be stored for up to eight hours in a syringe; however, total storage time for the reconstituted material must not exceed eight hours when exposed to normal indoor lighting.

3 DOSAGE FORMS AND STRENGTHS

For injection: Each single-dose vial of Bortezomib for Injection contains 1 mg or 2.5 mg of bortezomib as a sterile lyophilized white to off-white powder for reconstitution and withdrawal of the appropriate individual patient dose [see Dosage and Administration (2.10)].

4 CONTRAINDICATIONS

Bortezomib for Injection is contraindicated in patients with hypersensitivity (not including local reactions) to bortezomib, boron, or mannitol. Reactions have included anaphylactic reactions [see Adverse Reactions (6.1)].

Bortezomib for Injection is contraindicated for intrathecal administration. Fatal events have occurred with intrathecal administration of bortezomib products.

5 WARNINGS AND PRECAUTIONS

5.1 Peripheral Neuropathy

Bortezomib treatment causes a peripheral neuropathy that is predominantly sensory; however, cases of severe sensory and motor peripheral neuropathy have been reported. Patients with pre-existing symptoms (numbness, pain or a burning feeling in the feet or hands) and/or signs of peripheral neuropathy may experience worsening peripheral neuropathy (including ≥Grade 3) during treatment with Bortezomib for Injection. Patients should be monitored for symptoms of neuropathy, such as a burning sensation, hyperesthesia, hypoesthesia, paresthesia, discomfort, neuropathic pain or weakness. In the Phase 3 relapsed multiple myeloma trial comparing bortezomib subcutaneous vs intravenous, the incidence of Grade ≥2 peripheral neuropathy was 24% for subcutaneous and 39% for intravenous. Grade ≥3 peripheral neuropathy occurred in 6% of patients in the subcutaneous treatment group, compared with 15% in the intravenous treatment group [see Adverse Reactions (6.1)]. Starting Bortezomib for Injection subcutaneously may be considered for patients with pre-existing or at high risk of peripheral neuropathy.

Patients experiencing new or worsening peripheral neuropathy during Bortezomib for Injection therapy may require a decrease in the dose and/or a less dose-intense schedule [see Dosage and Administration (2.7)]. In the bortezomib vs dexamethasone Phase 3 relapsed multiple myeloma study, improvement in or resolution of peripheral neuropathy was reported in 48% of patients with ≥Grade 2 peripheral neuropathy following dose adjustment or interruption. Improvement in or resolution of peripheral neuropathy was reported in 73% of patients who discontinued due to Grade 2 neuropathy or who had ≥Grade 3 peripheral neuropathy in the Phase 2 multiple myeloma studies. The long-term outcome of peripheral neuropathy has not been studied in mantle cell lymphoma.

5.2 Hypotension

The incidence of hypotension (postural, orthostatic, and hypotension NOS) was 8% [see Adverse Reactions (6.1)]. These events are observed throughout therapy. Patients with a history of syncope, patients receiving medications known to be associated with hypotension, and patients who are dehydrated may be at increased risk of hypotension. Management of orthostatic/postural hypotension may include adjustment of antihypertensive medications, hydration, and administration of mineralocorticoids and/or sympathomimetics.

5.3 Cardiac Toxicity

Acute development or exacerbation of congestive heart failure and new onset of decreased left ventricular ejection fraction have occurred during bortezomib therapy, including reports in patients with no risk factors for decreased left ventricular ejection fraction [see Adverse Reactions (6.1)]. Patients with risk factors for, or existing heart disease should be frequently monitored. In the relapsed multiple myeloma study of bortezomib vs dexamethasone, the incidence of any treatment-related cardiac disorder was 8% and 5% in the bortezomib and dexamethasone groups, respectively. The incidence of adverse reactions suggestive of heart failure (acute pulmonary edema, pulmonary edema, cardiac failure, congestive cardiac failure, cardiogenic shock) was ≤1% for each individual reaction in the bortezomib group. In the dexamethasone group the incidence was ≤1% for cardiac failure and congestive cardiac failure; there were no reported reactions of acute pulmonary edema, pulmonary edema, or cardiogenic shock. There have been isolated cases of QT-interval prolongation in clinical studies; causality has not been established.

5.4 Pulmonary Toxicity

Acute Respiratory Distress Syndrome (ARDS) and acute diffuse infiltrative pulmonary disease of unknown etiology such as pneumonitis, interstitial pneumonia, lung infiltration have occurred in patients receiving bortezomib. Some of these events have been fatal.

In a clinical trial, the first two patients given high-dose cytarabine (2 g/m^2 per day) by continuous infusion with daunorubicin and bortezomib for relapsed acute myelogenous leukemia died of ARDS early in the course of therapy.

There have been reports of pulmonary hypertension associated with bortezomib administration in the absence of left heart failure or significant pulmonary disease.

In the event of new or worsening cardiopulmonary symptoms, consider interrupting Bortezomib for Injection until a prompt and comprehensive diagnostic evaluation is conducted.

5.5 Posterior Reversible Encephalopathy Syndrome (PRES)

Posterior Reversible Encephalopathy Syndrome (PRES; formerly termed Reversible Posterior Leukoencephalopathy Syndrome (RPLS)) has occurred in patients receiving bortezomib. PRES is a rare, reversible, neurological disorder which can present with seizure, hypertension, headache, lethargy, confusion, blindness, and other visual and neurological disturbances. Brain imaging, preferably MRI (Magnetic Resonance Imaging), is used to confirm the diagnosis. In patients developing PRES, discontinue Bortezomib for Injection. The safety of reinitiating Bortezomib for Injection therapy in patients previously experiencing PRES is not known.

5.6 Gastrointestinal Toxicity

Bortezomib treatment can cause nausea, diarrhea, constipation, and vomiting [see Adverse Reactions (6.1)] sometimes requiring use of antiemetic and antidiarrheal medications. Ileus can occur. Fluid and electrolyte replacement should be administered to prevent dehydration. Interrupt Bortezomib for Injection for severe symptoms.

5.7 Thrombocytopenia/Neutropenia

Bortezomib is associated with thrombocytopenia and neutropenia that follow a cyclical pattern with nadirs occurring following the last dose of each cycle and typically recovering prior to initiation of the subsequent cycle. The cyclical pattern of platelet and neutrophil decreases and recovery remain consistent in the studies of multiple myeloma and mantle cell lymphoma, with no evidence of cumulative thrombocytopenia or neutropenia in the treatment regimens studied.

Monitor complete blood counts (CBC) frequently during treatment with Bortezomib for Injection. Measure platelet counts prior to each dose of Bortezomib for Injection. Adjust dose/schedule for thrombocytopenia [see Dosage and Administration (2.6)]. Gastrointestinal and intracerebral hemorrhage has occurred during thrombocytopenia in association with bortezomib. Support with transfusions and supportive care, according to published guidelines.

In the single agent, relapsed multiple myeloma study of bortezomib vs dexamethasone, the mean platelet count nadir measured was approximately 40% of baseline. The severity of thrombocytopenia related to pretreatment platelet count is shown in Table 8. The incidence of bleeding (≥Grade 3) was 2% on the bortezomib arm and was <1% in the dexamethasone arm.

Table 8: Severity of Thrombocytopenia Related to Pretreatment Platelet Count in the Relapsed Multiple Myeloma Study of Bortezomib vs Dexamethasone
Pretreatment Platelet Count [A baseline platelet count of 50,000/µL was required for study eligibility] | Number of Patients (N=331) [Data were missing at baseline for one patient] | Number (%) of Patients with Platelet Count <10,000/µL | Number (%) of Patients with Platelet Count 10,000 to 25,000/µL
≥ 75,000/µL | 309 | 8 (3%) | 36 (12%)
≥ 50,000/µL to < 75,000/ µL | 14 | 2 (14%) | 11 (79%)
≥ 10,000/µL to < 50,000/ µL | 7 | 1 (14%) | 5 (71%)

In the combination study of bortezomib with rituximab, cyclophosphamide, doxorubicin and prednisone (VcR-CAP) in previously untreated mantle cell lymphoma patients, the incidence of thrombocytopenia (≥Grade 4) was 32% vs 1% for the rituximab, cyclophosphamide, doxorubicin, vincristine, and prednisone (R-CHOP) arm as shown in Table 12. The incidence of bleeding events (≥Grade 3) was 1.7% in the VcR-CAP arm (four patients) and was 1.2% in the R-CHOP arm (three patients).

Platelet transfusions were given to 23% of the patients in the VcR-CAP arm and 3% of the patients in the R-CHOP arm.

The incidence of neutropenia (≥Grade 4) was 70% in the VcR-CAP arm and was 52% in the R-CHOP arm. The incidence of febrile neutropenia (≥Grade 4) was 5% in the VcR-CAP arm and was 6% in the R-CHOP arm. Myeloid growth factor support was provided at a rate of 78% in the VcR-CAP arm and 61% in the R-CHOP arm.

5.8 Tumor Lysis Syndrome

Tumor lysis syndrome has been reported with bortezomib therapy. Patients at risk of tumor lysis syndrome are those with high tumor burden prior to treatment. Monitor patients closely and take appropriate precautions.

5.9 Hepatic Toxicity

Cases of acute liver failure have been reported in patients receiving multiple concomitant medications and with serious underlying medical conditions. Other reported hepatic reactions include hepatitis, increases in liver enzymes, and hyperbilirubinemia. Interrupt Bortezomib for Injection therapy to assess reversibility. There is limited rechallenge information in these patients.

5.10 Thrombotic Microangiopathy

Cases, sometimes fatal, of thrombotic microangiopathy, including thrombotic thrombocytopenic purpura/hemolytic uremic syndrome (TTP/HUS), have been reported in the postmarketing setting in patients who received bortezomib. Monitor for signs and symptoms of TTP/HUS. If the diagnosis is suspected, stop bortezomib and evaluate. If the diagnosis of TTP/HUS is excluded, consider restarting bortezomib. The safety of reinitiating Bortezomib for Injection therapy in patients previously experiencing TTP/HUS is not known.

5.11 Embryo-Fetal Toxicity

Based on the mechanism of action and findings in animals, Bortezomib for Injection can cause fetal harm when administered to a pregnant woman. Bortezomib administered to rabbits during organogenesis at a dose approximately 0.5 times the clinical dose of 1.3 mg/m^2 based on body surface area caused post-implantation loss and a decreased number of live fetuses [see Use in Specific Populations (8.1)].

Females of reproductive potential should avoid becoming pregnant while being treated with Bortezomib for Injection. Advise females of reproductive potential to use effective contraception during treatment with Bortezomib for Injection and for seven months following treatment. Advise males with female partners of reproductive potential to use effective contraception during treatment with Bortezomib for Injection and for four months following treatment. If Bortezomib for Injection is used during pregnancy or if the patient becomes pregnant during Bortezomib for Injection treatment, the patient should be apprised of the potential risk to the fetus [see Use in Specific Populations (8.1, 8.3), Nonclinical Toxicology (13.1)].

6 ADVERSE REACTIONS

The following clinically significant adverse reactions are also discussed in other sections of the labeling:

- Peripheral Neuropathy [see Warnings and Precautions (5.1)]
- Hypotension [see Warnings and Precautions (5.2)]
- Cardiac Toxicity [see Warnings and Precautions (5.3)]
- Pulmonary Toxicity [see Warnings and Precautions (5.4)]
- Posterior Reversible Encephalopathy Syndrome (PRES) [see Warnings and Precautions (5.5)]
- Gastrointestinal Toxicity [see Warnings and Precautions (5.6)]
- Thrombocytopenia/Neutropenia [see Warnings and Precautions (5.7)]
- Tumor Lysis Syndrome [see Warnings and Precautions (5.8)]
- Hepatic Toxicity [see Warnings and Precautions (5.9)]
- Thrombotic Microangiopathy [see Warnings and Precautions (5.10)]

6.1 Clinical Trials Experience

Because clinical trials are conducted under widely varying conditions, adverse reaction rates observed in the clinical trials of a drug cannot be directly compared to rates in the clinical trials of another drug and may not reflect the rates observed in clinical practice.

Summary of Clinical Trial in Patients with Previously Untreated Multiple Myeloma

Table 9 describes safety data from 340 patients with previously untreated multiple myeloma who received bortezomib (1.3 mg/m^2) administered intravenously in combination with melphalan (9 mg/m^2) and prednisone (60 mg/m^2) in a prospective randomized study.

The safety profile of bortezomib in combination with melphalan/prednisone is consistent with the known safety profiles of both bortezomib and melphalan/prednisone.

Table 9: Most Commonly Reported Adverse Reactions (≥10% in the Bortezomib, Melphalan and Prednisone Arm) with Grades 3 and ≥4 Intensity in the Previously Untreated Multiple Myeloma Study
 | Bortezomib, Melphalan and Prednisone (n = 340) |  |  | Melphalan and Prednisone (n = 337)
Body System | Total | Toxicity Grade, n (%) |  | Total | Toxicity Grade, n (%)
Adverse Reaction | n (%) | 3 | ≥4 | n (%) | 3 | ≥4
Blood and Lymphatic System Disorders
Thrombocytopenia | 164 (48) | 60 (18) | 57 (17) | 140 (42) | 48 (14) | 39 (12)
Neutropenia | 160 (47) | 101 (30) | 33 (10) | 143 (42) | 77 (23) | 42 (12)
Anemia | 109 (32) | 41 (12) | 4 (1) | 156 (46) | 61 (18) | 18 (5)
Leukopenia | 108 (32) | 64 (19) | 8 (2) | 93 (28) | 53 (16) | 11 (3)
Lymphopenia | 78 (23) | 46 (14) | 17 (5) | 51 (15) | 26 (8) | 7 (2)
Gastrointestinal Disorders
Nausea | 134 (39) | 10 (3) | 0 | 70 (21) | 1 (<1) | 0
Diarrhea | 119 (35) | 19 (6) | 2 (1) | 20 (6) | 1 (<1) | 0
Vomiting | 87 (26) | 13 (4) | 0 | 41 (12) | 2 (1) | 0
Constipation | 77 (23) | 2 (1) | 0 | 14 (4) | 0 | 0
Abdominal pain upper | 34 (10) | 1 (<1) | 0 | 20 (6) | 0 | 0
Nervous System Disorders
Peripheral neuropathy [Represents High Level Term Peripheral Neuropathies NEC] | 156 (46) | 42 (12) | 2 (1) | 4 (1) | 0 | 0
Neuralgia | 117 (34) | 27 (8) | 2 (1) | 1 (<1) | 0 | 0
Paresthesia | 42 (12) | 6 (2) | 0 | 4 (1) | 0 | 0
General Disorders and Administration Site Conditions
Fatigue | 85 (25) | 19 (6) | 2 (1) | 48 (14) | 4 (1) | 0
Asthenia | 54 (16) | 18 (5) | 0 | 23 (7) | 3 (1) | 0
Pyrexia | 53 (16) | 4 (1) | 0 | 19 (6) | 1 (<1) | 1 (<1)
Infections and Infestations
Herpes Zoster | 39 (11) | 11 (3) | 0 | 9 (3) | 4 (1) | 0
Metabolism and Nutrition Disorders
Anorexia | 64 (19) | 6 (2) | 0 | 19 (6) | 0 | 0
Skin and Subcutaneous Tissue Disorders
Rash | 38 (11) | 2 (1) | 0 | 7 (2) | 0 | 0
Psychiatric Disorders
Insomnia | 35 (10) | 1 (<1) | 0 | 21 (6) | 0 | 0

Relapsed Multiple Myeloma Randomized Study of Bortezomib vs Dexamethasone

The safety data described below and in Table 10 reflect exposure to either bortezomib (n=331) or dexamethasone (n=332) in a study of patients with relapsed multiple myeloma. Bortezomib was administered intravenously at doses of 1.3 mg/m^2 twice weekly for two out of three weeks (21 day cycle). After eight 21 day cycles patients continued therapy for three 35 day cycles on a weekly schedule. Duration of treatment was up to 11 cycles (nine months) with a median duration of six cycles (4.1 months). For inclusion in the trial, patients must have had measurable disease and one to three prior therapies. There was no upper age limit for entry. Creatinine clearance could be as low as 20 mL/min and bilirubin levels as high as 1.5 times the upper limit of normal. The overall frequency of adverse reactions was similar in men and women, and in patients <65 and ≥65 years of age. Most patients were Caucasian [see Clinical Studies (14.1)].

Among the 331 bortezomib-treated patients, the most commonly reported (>20%) adverse reactions overall were nausea (52%), diarrhea (52%), fatigue (39%), peripheral neuropathies (35%), thrombocytopenia (33%), constipation (30%), vomiting (29%), and anorexia (21%). The most commonly reported (>20%) adverse reaction reported among the 332 patients in the dexamethasone group was fatigue (25%). Eight percent (8%) of patients in the bortezomib-treated arm experienced a Grade 4 adverse reaction; the most common reactions were thrombocytopenia (4%) and neutropenia (2%). Nine percent (9%) of dexamethasone-treated patients experienced a Grade 4 adverse reaction. All individual dexamethasone-related Grade 4 adverse reactions were less than 1%.

Serious Adverse Reactions and Adverse Reactions Leading to Treatment Discontinuation in the Relapsed Multiple Myeloma Study of Bortezomib vs Dexamethasone

Serious adverse reactions are defined as any reaction that results in death, is life-threatening, requires hospitalization or prolongs a current hospitalization, results in a significant disability, or is deemed to be an important medical event. A total of 80 (24%) patients from the bortezomib treatment arm experienced a serious adverse reaction during the study, as did 83 (25%) dexamethasone-treated patients. The most commonly reported serious adverse reactions in the bortezomib treatment arm were diarrhea (3%), dehydration, herpes zoster, pyrexia, nausea, vomiting, dyspnea, and thrombocytopenia (2% each). In the dexamethasone treatment group, the most commonly reported serious adverse reactions were pneumonia (4%), hyperglycemia (3%), pyrexia, and psychotic disorder (2% each).

A total of 145 patients, including 84 (25%) of 331 patients in the bortezomib treatment group and 61 (18%) of 332 patients in the dexamethasone treatment group were discontinued from treatment due to adverse reactions. Among the 331 bortezomib-treated patients, the most commonly reported adverse reaction leading to discontinuation was peripheral neuropathy (8%). Among the 332 patients in the dexamethasone group, the most commonly reported adverse reactions leading to treatment discontinuation were psychotic disorder and hyperglycemia (2% each).

Four deaths were considered to be bortezomib-related in this relapsed multiple myeloma study: one case each of cardiogenic shock, respiratory insufficiency, congestive heart failure and cardiac arrest. Four deaths were considered dexamethasone-related: two cases of sepsis, one case of bacterial meningitis, and one case of sudden death at home.

Most Commonly Reported Adverse Reactions in the Relapsed Multiple Myeloma Study of Bortezomib vs Dexamethasone

The most common adverse reactions from the relapsed multiple myeloma study are shown in Table 10. All adverse reactions with incidence ≥10% in the bortezomib arm are included.

Table 10: Most Commonly Reported Adverse Reactions (≥10% in Bortezomib Arm), with Grades 3 and 4 Intensity in the Relapsed Multiple Myeloma Study of Bortezomib vs Dexamethasone (N=663)
 | Bortezomib (N = 331) |  |  | Dexamethasone (N = 332)
Adverse Reactions | All | Grade 3 | Grade 4 | All | Grade 3 | Grade 4
Any Adverse Reactions | 324 (98) | 193 (58) | 28 (8) | 297 (89) | 110 (33) | 29 (9)
Nausea | 172 (52) | 8 (2) | 0 | 31 (9) | 0 | 0
Diarrhea NOS | 171 (52) | 22 (7) | 0 | 36 (11) | 2 (<1) | 0
Fatigue | 130 (39) | 15 (5) | 0 | 82 (25) | 8 (2) | 0
Peripheral neuropathies [Represents High Level Term Peripheral Neuropathies NEC] | 115 (35) | 23 (7) | 2 (<1) | 14 (4) | 0 | 1 (< 1)
Thrombocytopenia | 109 (33) | 80 (24) | 12 (4) | 11 (3) | 5 (2) | 1 (< 1)
Constipation | 99 (30) | 6 (2) | 0 | 27 (8) | 1 (<1) | 0
Vomiting NOS | 96 (29) | 8 (2) | 0 | 10 (3) | 1 (<1) | 0
Anorexia | 68 (21) | 8 (2) | 0 | 8 (2) | 1 (<1) | 0
Pyrexia | 66 (20) | 2 (<1) | 0 | 21 (6) | 3 (<1) | 1 (< 1)
Paresthesia | 64 (19) | 5 (2) | 0 | 24 (7) | 0 | 0
Anemia NOS | 63 (19) | 20 (6) | 1 (<1) | 21 (6) | 8 (2) | 0
Headache NOS | 62 (19) | 3 (<1) | 0 | 23 (7) | 1 (<1) | 0
Neutropenia | 58 (18) | 37 (11) | 8 (2) | 1 (<1) | 1 (<1) | 0
Rash NOS | 43 (13) | 3 (<1) | 0 | 7 (2) | 0 | 0
Appetite decreased NOS | 36 (11) | 0 | 0 | 12 (4) | 0 | 0
Dyspnea NOS | 35 (11) | 11 (3) | 1 (<1) | 37 (11) | 7 (2) | 1 (< 1)
Abdominal pain NOS | 35 (11) | 5 (2) | 0 | 7 (2) | 0 | 0
Weakness | 34 (10) | 10 (3) | 0 | 28 (8) | 8 (2) | 0

Safety Experience from the Phase 2 Open-Label Extension Study in Relapsed Multiple Myeloma

In the Phase 2 extension study of 63 patients, no new cumulative or new long-term toxicities were observed with prolonged bortezomib treatment. These patients were treated for a total of 5.3 to 23 months, including time on bortezomib in the prior bortezomib study [see Clinical Studies (14.1)].

Safety Experience from the Phase 3 Open-Label Study of Bortezomib Subcutaneous vs Intravenous in Relapsed Multiple Myeloma

The safety and efficacy of bortezomib administered subcutaneously were evaluated in one Phase 3 study at the recommended dose of 1.3 mg/m^2. This was a randomized, comparative study of bortezomib subcutaneous vs intravenous in 222 patients with relapsed multiple myeloma. The safety data described below and in Table 11 reflect exposure to either bortezomib subcutaneous (N=147) or bortezomib intravenous (N=74) [see Clinical Studies (14.1)].

Table 11: Most Commonly Reported Adverse Reactions (≥10%), with Grade 3 and ≥4 Intensity in the Relapsed Multiple Myeloma Study (N=221) of Bortezomib Subcutaneous vs Intravenous
 | Subcutaneous (N = 147) |  |  | Intravenous (N = 74)
Body System | Total | Toxicity Grade, n (%) |  | Total | Toxicity Grade, n (%)
Adverse Reaction | n (%) | 3 | ≥4 | n (%) | 3 | ≥4
Blood and Lymphatic System Disorders
Anemia | 28 (19) | 8 (5) | 0 | 17 (23) | 3 (4) | 0
Leukopenia | 26 (18) | 8 (5) | 0 | 15 (20) | 4 (5) | 1 (1)
Neutropenia | 34 (23) | 15 (10) | 4 (3) | 20 (27) | 10 (14) | 3 (4)
Thrombocytopenia | 44 (30) | 7 (5) | 5 (3) | 25 (34) | 7 (9) | 5 (7)
Gastrointestinal Disorders
Diarrhea | 28 (19) | 1 (1) | 0 | 21 (28) | 3 (4) | 0
Nausea | 24 (16) | 0 | 0 | 10 (14) | 0 | 0
Vomiting | 13 (9) | 3 (2) | 0 | 8 (11) | 0 | 0
General Disorders and Administration Site Conditions
Asthenia | 10 (7) | 1 (1) | 0 | 12 (16) | 4 (5) | 0
Fatigue | 11 (7) | 3 (2) | 0 | 11 (15) | 3 (4) | 0
Pyrexia | 18 (12) | 0 | 0 | 6 (8) | 0 | 0
Nervous System Disorders
Neuralgia | 34 (23) | 5 (3) | 0 | 17 (23) | 7 (9) | 0
Peripheral neuropathies [Represents High Level Term Peripheral Neuropathies NEC] | 55 (37) | 8 (5) | 1 (1) | 37 (50) | 10 (14) | 1 (1)
Note: Safety population: 147 patients in the subcutaneous treatment group and 74 patients in the intravenous treatment group who received at least one dose of study medication

In general, safety data were similar for the subcutaneous and intravenous treatment groups. Differences were observed in the rates of some Grade ≥3 adverse reactions. Differences of ≥5% were reported in neuralgia (3% subcutaneous vs 9% intravenous), peripheral neuropathies (6% subcutaneous vs 15% intravenous), neutropenia (13% subcutaneous vs 18% intravenous), and thrombocytopenia (8% subcutaneous vs 16% intravenous).

A local reaction was reported in 6% of patients in the subcutaneous group, mostly redness. Only two (1%) patients were reported as having severe reactions, one case of pruritus and one case of redness. Local reactions led to reduction in injection concentration in one patient and drug discontinuation in one patient. Local reactions resolved in a median of six days.

Dose reductions occurred due to adverse reactions in 31% of patients in the subcutaneous treatment group compared with 43% of the intravenously-treated patients. The most common adverse reactions leading to a dose reduction included peripheral sensory neuropathy (17% in the subcutaneous treatment group compared with 31% in the intravenous treatment group); and neuralgia (11% in the subcutaneous treatment group compared with 19% in the intravenous treatment group).

Serious Adverse Reactions and Adverse Reactions Leading to Treatment Discontinuation in the Relapsed Multiple Myeloma Study of Bortezomib Subcutaneous vs Intravenous

The incidence of serious adverse reactions was similar for the subcutaneous treatment group (20%) and the intravenous treatment group (19%). The most commonly reported serious adverse reactions in the subcutaneous treatment arm were pneumonia and pyrexia (2% each). In the intravenous treatment group, the most commonly reported serious adverse reactions were pneumonia, diarrhea, and peripheral sensory neuropathy (3% each).

In the subcutaneous treatment group, 27 patients (18%) discontinued study treatment due to an adverse reaction compared with 17 patients (23%) in the intravenous treatment group. Among the 147 subcutaneously-treated patients, the most commonly reported adverse reactions leading to discontinuation were peripheral sensory neuropathy (5%) and neuralgia (5%). Among the 74 patients in the intravenous treatment group, the most commonly reported adverse reactions leading to treatment discontinuation were peripheral sensory neuropathy (9%) and neuralgia (9%).

Two patients (1%) in the subcutaneous treatment group and one (1%) patient in the intravenous treatment group died due to an adverse reaction during treatment. In the subcutaneous group the causes of death were one case of pneumonia and one case of sudden death. In the intravenous group the cause of death was coronary artery insufficiency.

Safety Experience from the Clinical Trial in Patients with Previously Untreated Mantle Cell Lymphoma

Table 12 describes safety data from 240 patients with previously untreated mantle cell lymphoma who received bortezomib (1.3 mg/m^2) administered intravenously in combination with rituximab (375 mg/m^2), cyclophosphamide (750 mg/m^2), doxorubicin (50 mg/m^2), and prednisone (100 mg/m^2) (VcR-CAP) in a prospective randomized study.

Infections were reported for 31% of patients in the VcR-CAP arm and 23% of the patients in the comparator (rituximab, cyclophosphamide, doxorubicin, vincristine, and prednisone [R-CHOP]) arm, including the predominant preferred term of pneumonia (VcR-CAP 8% vs R-CHOP 5%).

Table 12: Most Commonly Reported Adverse Reactions (≥5%) with Grades 3 and ≥4 Intensity in the Previously Untreated Mantle Cell Lymphoma Study
 | VcR-CAP (N = 240) |  |  | R-CHOP (N = 242)
Body System | All | Toxicity Grade 3 | Toxicity Grade ≥4 | All | Toxicity Grade 3 | Toxicity Grade ≥4
Adverse Reactions | n (%) | n (%) | n (%) | n (%) | n (%) | n (%)
Blood and Lymphatic System Disorders
Neutropenia | 209 (87) | 32 (13) | 168 (70) | 172 (71) | 31 (13) | 125 (52)
Leukopenia | 116 (48) | 34 (14) | 69 (29) | 87 (36) | 39 (16) | 27 (11)
Anemia | 106 (44) | 27 (11) | 4 (2) | 71 (29) | 23 (10) | 4 (2)
Thrombocytopenia | 172 (72) | 59 (25) | 76 (32) | 42 (17) | 9 (4) | 3 (1)
Febrile neutropenia | 41 (17) | 24 (10) | 12 (5) | 33 (14) | 17 (7) | 15 (6)
Lymphopenia | 68 (28) | 25 (10) | 36 (15) | 28 (12) | 15 (6) | 2 (1)
Nervous System Disorders
Peripheral
neuropathy [Represents High Level Term Peripheral Neuropathies NEC.] | 71 (30) | 17 (7) | 1 (<1) | 65 (27) | 10 (4) | 0
Hypoesthesia | 14 (6) | 3 (1) | 0 | 13 (5) | 0 | 0
Paresthesia | 14 (6) | 2 (1) | 0 | 11 (5) | 0 | 0
Neuralgia | 25 (10) | 9 (4) | 0 | 1 (<1) | 0 | 0
General Disorders and Administration Site Conditions
Fatigue | 43 (18) | 11 (5) | 1 (<1) | 38 (16) | 5 (2) | 0
Pyrexia | 48 (20) | 7 (3) | 0 | 23 (10) | 5 (2) | 0
Asthenia | 29 (12) | 4 (2) | 1 (<1) | 18 (7) | 1 (<1) | 0
Edema peripheral | 16 (7) | 1 (<1) | 0 | 13 (5) | 0 | 0
Gastrointestinal Disorders
Nausea | 54 (23) | 1 (<1) | 0 | 28 (12) | 0 | 0
Constipation | 42 (18) | 1 (<1) | 0 | 22 (9) | 2 (1) | 0
Stomatitis | 20 (8) | 2 (1) | 0 | 19 (8) | 0 | 1 (<1)
Diarrhea | 59 (25) | 11 (5) | 0 | 11 (5) | 3 (1) | 1 (<1)
Vomiting | 24 (10) | 1 (<1) | 0 | 8 (3) | 0 | 0
Abdominal distension | 13 (15) | 0 | 0 | 4 (2) | 0 | 0
Infections and Infestations
Pneumonia | 20 (8) | 8 (3) | 5 (2) | 11 (5) | 5 (2) | 3 (1)
Skin and Subcutaneous Tissue Disorders
Alopecia | 31 (13) | 1 (<1) | 1 (<1) | 33 (14) | 4 (2) | 0
Metabolism and Nutrition Disorders
Hyperglycemia | 10 (4) | 1 (<1) | 0 | 17 (7) | 10 (4) | 0
Decreased appetite | 36 (15) | 2 (1) | 0 | 15 (6) | 1 (<1) | 0
Vascular Disorders
Hypertension | 15 (6) | 1 (<1) | 0 | 3 (1) | 0 | 0
Psychiatric Disorders
Insomnia | 16 (7) | 1 (<1) | 0 | 8 (3) | 0 | 0
Key: R-CHOP = rituximab, cyclophosphamide, doxorubicin, vincristine, and prednisone; VcR-CAP = bortezomib, rituximab, cyclophosphamide, doxorubicin, and prednisone.

The incidence of herpes zoster reactivation was 4.6% in the VcR-CAP arm and 0.8% in the R-CHOP arm. Antiviral prophylaxis was mandated by protocol amendment.

The incidences of Grade ≥3 bleeding events were similar between the two arms (four patients in the VcR-CAP arm and three patients in the R-CHOP arm). All of the Grade ≥3 bleeding events resolved without sequelae in the VcR-CAP arm.

Adverse reactions leading to discontinuation occurred in 8% of patients in VcR-CAP group and 6% of patients in R-CHOP group. In the VcR-CAP group, the most commonly reported adverse reaction leading to discontinuation was peripheral sensory neuropathy (1%; three patients). The most commonly reported adverse reaction leading to discontinuation in the R-CHOP group was febrile neutropenia (<1%; two patients).

Integrated Summary of Safety (Relapsed Multiple Myeloma and Relapsed Mantle Cell Lymphoma)

Safety data from Phase 2 and 3 studies of single agent bortezomib 1.3 mg/m^2/dose twice weekly for two weeks followed by a ten day rest period in 1163 patients with previously-treated multiple myeloma (N=1008) and previously-treated mantle cell lymphoma (N=155) were integrated and tabulated. This analysis does not include data from the Phase 3 open-label study of bortezomib subcutaneous vs intravenous in relapsed multiple myeloma. In the integrated studies, the safety profile of bortezomib was similar in patients with multiple myeloma and mantle cell lymphoma.

In the integrated analysis, the most commonly reported (>20%) adverse reactions were nausea (49%), diarrhea (46%), asthenic conditions including fatigue (41%) and weakness (11%), peripheral neuropathies (38%), thrombocytopenia (32%), vomiting (28%), constipation (25%), and pyrexia (21%). Eleven percent (11%) of patients experienced at least one episode of ≥Grade 4 toxicity, most commonly thrombocytopenia (4%) and neutropenia (2%).

In the Phase 2 relapsed multiple myeloma clinical trials of bortezomib administered intravenously, local skin irritation was reported in 5% of patients, but extravasation of bortezomib was not associated with tissue damage.

Serious Adverse Reactions and Adverse Reactions Leading to Treatment Discontinuation in the Integrated Summary of Safety

A total of 26% of patients experienced a serious adverse reaction during the studies. The most commonly reported serious adverse reactions included diarrhea, vomiting and pyrexia (3% each), nausea, dehydration, and thrombocytopenia (2% each) and pneumonia, dyspnea, peripheral neuropathies, and herpes zoster (1% each).

Adverse reactions leading to discontinuation occurred in 22% of patients. The reasons for discontinuation included peripheral neuropathy (8%), and fatigue, thrombocytopenia, and diarrhea (2% each).

In total, 2% of the patients died and the cause of death was considered by the investigator to be possibly related to study drug: including reports of cardiac arrest, congestive heart failure, respiratory failure, renal failure, pneumonia and sepsis.

Most Commonly Reported Adverse Reactions in the Integrated Summary of Safety

The most common adverse reactions are shown in Table 13. All adverse reactions occurring at ≥10% are included. In the absence of a randomized comparator arm, it is often not possible to distinguish between adverse events that are drug-caused and those that reflect the patient's underlying disease. Please see the discussion of specific adverse reactions that follows.

Table 13: Most Commonly Reported (≥ 10% Overall) Adverse Reactions in Integrated Analyses of Relapsed Multiple Myeloma and Relapsed Mantle Cell Lymphoma Studies Using the 1.3 mg/m^2 Dose (N=1163)
 | All Patients (N=1163) |  | Multiple Myeloma (N=1008) |  | Mantle Cell Lymphoma (N=155)
Adverse Reactions | All | ≥Grade 3 | All | ≥Grade 3 | All | ≥Grade 3
Nausea | 567 (49) | 36 (3) | 511 (51) | 32 (3) | 56 (36) | 4 (3)
Diarrhea NOS | 530 (46) | 83 (7) | 470 (47) | 72 (7) | 60 (39) | 11 (7)
Fatigue | 477 (41) | 86 (7) | 396 (39) | 71 (7) | 81 (52) | 15 (10)
Peripheral neuropathies [Represents High Level Term Peripheral Neuropathies NEC] | 443 (38) | 129 (11) | 359 (36) | 110 (11) | 84 (54) | 19 (12)
Thrombocytopenia | 369 (32) | 295 (25) | 344 (34) | 283 (28) | 25 (16) | 12 (8)
Vomiting NOS | 321 (28) | 44 (4) | 286 (28) | 40 (4) | 35 (23) | 4 (3)
Constipation | 296 (25) | 17 (1) | 244 (24) | 14 (1) | 52 (34) | 3 (2)
Pyrexia | 249 (21) | 16 (1) | 233 (23) | 15 (1) | 16 (10) | 1 (<1)
Anorexia | 227 (20) | 19 (2) | 205 (20) | 16 (2) | 22 (14) | 3 (2)
Anemia NOS | 209 (18) | 65 (6) | 190 (19) | 63 (6) | 19 (12) | 2 (1)
Headache NOS | 175 (15) | 8 (<1) | 160 (16) | 8 (<1) | 15 (10) | 0
Neutropenia | 172 (15) | 121 (10) | 164 (16) | 117 (12) | 8 (5) | 4 (3)
Rash NOS | 156 (13) | 8 (<1) | 120 (12) | 4 (<1) | 36 (23) | 4 (3)
Paresthesia | 147 (13) | 9 (<1) | 136 (13) | 8 (<1) | 11 (7) | 1 (<1)
Dizziness (excl vertigo) | 129 (11) | 13 (1) | 101 (10) | 9 (<1) | 28 (18) | 4 (3)
Weakness | 124 (11) | 31 (3) | 106 (11) | 28 (3) | 18 (12) | 3 (2)

Description of Selected Adverse Reactions from the Integrated Phase 2 and Phase 3 Relapsed Multiple Myeloma and Phase 2 Relapsed Mantle Cell Lymphoma Studies

Gastrointestinal Toxicity

A total of 75% of patients experienced at least one gastrointestinal disorder. The most common gastrointestinal disorders included nausea, diarrhea, constipation, vomiting, and appetite decreased. Other gastrointestinal disorders included dyspepsia and dysgeusia. Grade 3 adverse reactions occurred in 14% of patients; ≥Grade 4 adverse reactions were ≤1%. Gastrointestinal adverse reactions were considered serious in 7% of patients. Four percent (4%) of patients discontinued due to a gastrointestinal adverse reaction. Nausea was reported more often in patients with multiple myeloma (51%) compared to patients with mantle cell lymphoma (36%).

Thrombocytopenia

Across the studies, bortezomib-associated thrombocytopenia was characterized by a decrease in platelet count during the dosing period (Days 1 to 11) and a return toward baseline during the ten day rest period during each treatment cycle. Overall, thrombocytopenia was reported in 32% of patients. Thrombocytopenia was Grade 3 in 22%, ≥Grade 4 in 4%, and serious in 2% of patients, and the reaction resulted in bortezomib discontinuation in 2% of patients [see Warnings and Precautions (5.7)]. Thrombocytopenia was reported more often in patients with multiple myeloma (34%) compared to patients with mantle cell lymphoma (16%). The incidence of ≥Grade 3 thrombocytopenia also was higher in patients with multiple myeloma (28%) compared to patients with mantle cell lymphoma (8%).

Peripheral Neuropathy

Overall, peripheral neuropathies occurred in 38% of patients. Peripheral neuropathy was Grade 3 for 11% of patients and ≥Grade 4 for <1% of patients. Eight percent (8%) of patients discontinued bortezomib due to peripheral neuropathy. The incidence of peripheral neuropathy was higher among patients with mantle cell lymphoma (54%) compared to patients with multiple myeloma (36%).

In the bortezomib vs dexamethasone Phase 3 relapsed multiple myeloma study, among the 62 bortezomib-treated patients who experienced ≥Grade 2 peripheral neuropathy and had dose adjustments, 48% had improved or resolved with a median of 3.8 months from first onset.

In the Phase 2 relapsed multiple myeloma studies, among the 30 patients who experienced Grade 2 peripheral neuropathy resulting in discontinuation or who experienced ≥Grade 3 peripheral neuropathy, 73% reported improvement or resolution with a median time of 47 days to improvement of one grade or more from the last dose of bortezomib.

Hypotension

The incidence of hypotension (postural, orthostatic and hypotension NOS) was 8% in patients treated with bortezomib. Hypotension was Grade 1 or 2 in the majority of patients and Grade 3 in 2% and ≥Grade 4 in <1%. Two percent (2%) of patients had hypotension reported as a serious adverse reaction, and 1% discontinued due to hypotension. The incidence of hypotension was similar in patients with multiple myeloma (8%) and those with mantle cell lymphoma (9%). In addition, <1% of patients experienced hypotension associated with a syncopal reaction.

Neutropenia

Neutrophil counts decreased during the bortezomib dosing period (Days 1 to 11) and returned toward baseline during the ten day rest period during each treatment cycle. Overall, neutropenia occurred in 15% of patients and was Grade 3 in 8% of patients and ≥Grade 4 in 2%. Neutropenia was reported as a serious adverse reaction in <1% of patients and <1% of patients discontinued due to neutropenia. The incidence of neutropenia was higher in patients with multiple myeloma (16%) compared to patients with mantle cell lymphoma (5%). The incidence of ≥Grade 3 neutropenia also was higher in patients with multiple myeloma (12%) compared to patients with mantle cell lymphoma (3%).

Asthenic Conditions (Fatigue, Malaise, Weakness, Asthenia)

Asthenic conditions were reported in 54% of patients. Fatigue was reported as Grade 3 in 7% and ≥Grade 4 in <1% of patients. Asthenia was reported as Grade 3 in 2% and ≥Grade 4 in <1% of patients. Two percent (2%) of patients discontinued treatment due to fatigue and <1% due to weakness and asthenia. Asthenic conditions were reported in 53% of patients with multiple myeloma and 59% of patients with mantle cell lymphoma.

Pyrexia

Pyrexia (>38°C) was reported as an adverse reaction for 21% of patients. The reaction was Grade 3 in 1% and ≥Grade 4 in <1%. Pyrexia was reported as a serious adverse reaction in 3% of patients and led to bortezomib discontinuation in <1% of patients. The incidence of pyrexia was higher among patients with multiple myeloma (23%) compared to patients with mantle cell lymphoma (10%). The incidence of ≥Grade 3 pyrexia was 1% in patients with multiple myeloma and <1% in patients with mantle cell lymphoma.

Herpes Virus Infection

Consider using antiviral prophylaxis in subjects being treated with Bortezomib for Injection. In the randomized studies in previously untreated and relapsed multiple myeloma, herpes zoster reactivation was more common in subjects treated with bortezomib (ranging between 6% to 11%) than in the control groups (3% to 4%). Herpes simplex was seen in 1% to 3% in subjects treated with bortezomib and 1% to 3% in the control groups. In the previously untreated multiple myeloma study, herpes zoster virus reactivation in the bortezomib, melphalan and prednisone arm was less common in subjects receiving prophylactic antiviral therapy (3%) than in subjects who did not receive prophylactic antiviral therapy (17%).

Retreatment in Relapsed Multiple Myeloma

A single-arm trial was conducted in 130 patients with relapsed multiple myeloma to determine the efficacy and safety of retreatment with intravenous bortezomib. The safety profile of patients in this trial is consistent with the known safety profile of bortezomib-treated patients with relapsed multiple myeloma as demonstrated in Tables 10, 11, and 13; no cumulative toxicities were observed upon retreatment. The most common adverse drug reaction was thrombocytopenia which occurred in 52% of the patients. The incidence of ≥Grade 3 thrombocytopenia was 24%. Peripheral neuropathy occurred in 28% of patients, with the incidence of ≥Grade 3 peripheral neuropathy reported at 6%. The incidence of serious adverse reactions was 12.3%. The most commonly reported serious adverse reactions were thrombocytopenia (3.8%), diarrhea (2.3%), and herpes zoster and pneumonia (1.5% each).

Adverse reactions leading to discontinuation occurred in 13% of patients. The reasons for discontinuation included peripheral neuropathy (5%) and diarrhea (3%).

Two deaths considered to be bortezomib-related occurred within 30 days of the last bortezomib dose; one in a patient with cerebrovascular accident and one in a patient with sepsis.

Additional Adverse Reactions from Clinical Studies

The following clinically important serious adverse reactions that are not described above have been reported in clinical trials in patients treated with bortezomib administered as monotherapy or in combination with other chemotherapeutics. These studies were conducted in patients with hematological malignancies and in solid tumors.

Blood and Lymphatic System Disorders: Anemia, disseminated intravascular coagulation, febrile neutropenia, lymphopenia, leukopenia

Cardiac Disorders: Angina pectoris, atrial fibrillation aggravated, atrial flutter, bradycardia, sinus arrest, cardiac amyloidosis, complete atrioventricular block, myocardial ischemia, myocardial infarction, pericarditis, pericardial effusion, Torsades de pointes, ventricular tachycardia

Ear and Labyrinth Disorders: Hearing impaired, vertigo

Eye Disorders: Diplopia and blurred vision, conjunctival infection, irritation

Gastrointestinal Disorders: Abdominal pain, ascites, dysphagia, fecal impaction, gastroenteritis, gastritis hemorrhagic, hematemesis, hemorrhagic duodenitis, ileus paralytic, large intestinal obstruction, paralytic intestinal obstruction, peritonitis, small intestinal obstruction, large intestinal perforation, stomatitis, melena, pancreatitis acute, oral mucosal petechiae, gastroesophageal reflux

General Disorders and Administration Site Conditions: Chills, edema, edema peripheral, injection site erythema, neuralgia, injection site pain, irritation, malaise, phlebitis

Hepatobiliary Disorders: Cholestasis, hepatic hemorrhage, hyperbilirubinemia, portal vein thrombosis, hepatitis, liver failure

Immune System Disorders: Anaphylactic reaction, drug hypersensitivity, immune complex mediated hypersensitivity, angioedema, laryngeal edema

Infections and Infestations: Aspergillosis, bacteremia, bronchitis, urinary tract infection, herpes viral infection, listeriosis, nasopharyngitis, pneumonia, respiratory tract infection, septic shock, toxoplasmosis, oral candidiasis, sinusitis, catheter-related infection

Injury, Poisoning and Procedural Complications: Catheter-related complication, skeletal fracture, subdural hematoma

Investigations: Weight decreased

Metabolism and Nutrition Disorders: Dehydration, hypocalcemia, hyperuricemia, hypokalemia, hyperkalemia, hyponatremia, hypernatremia

Musculoskeletal and Connective Tissue Disorders: Arthralgia, back pain, bone pain, myalgia, pain in extremity

Nervous System Disorders: Ataxia, coma, dizziness, dysarthria, dysesthesia, dysautonomia, encephalopathy, cranial palsy, grand mal convulsion, headache, hemorrhagic stroke, motor dysfunction, neuralgia, spinal cord compression, paralysis, postherpetic neuralgia, transient ischemic attack

Psychiatric Disorders: Agitation, anxiety, confusion, insomnia, mental status change, psychotic disorder, suicidal ideation

Renal and Urinary Disorders: Calculus renal, bilateral hydronephrosis, bladder spasm, hematuria, hemorrhagic cystitis, urinary incontinence, urinary retention, renal failure (acute and chronic), glomerular nephritis proliferative

Respiratory, Thoracic and Mediastinal Disorders: Acute respiratory distress syndrome, aspiration pneumonia, atelectasis, chronic obstructive airways disease exacerbated, cough, dysphagia, dyspnea, dyspnea exertional, epistaxis, hemoptysis, hypoxia, lung infiltration, pleural effusion, pneumonitis, respiratory distress, pulmonary hypertension

Skin and Subcutaneous Tissue Disorders: Urticaria, face edema, rash (which may be pruritic), leukocytoclastic vasculitis, pruritus

Vascular Disorders: Cerebrovascular accident, cerebral hemorrhage, deep venous thrombosis, hypertension, peripheral embolism, pulmonary embolism, pulmonary hypertension

6.2 Postmarketing Experience

The following adverse reactions have been identified from the worldwide postmarketing experience with bortezomib. Because these reactions are reported voluntarily from a population of uncertain size, it is not always possible to reliably estimate their frequency or establish a causal relationship to drug exposure:

Cardiac Disorders: Cardiac tamponade

Ear and Labyrinth Disorders: Deafness bilateral

Eye Disorders: Optic neuropathy, blindness, chalazion/blepharitis

Gastrointestinal Disorders: Ischemic colitis

Infections and Infestations: Progressive multifocal leukoencephalopathy (PML), ophthalmic herpes, herpes meningoencephalitis

Nervous System Disorders: Posterior reversible encephalopathy syndrome (PRES, formerly RPLS), Guillain-Barré syndrome, demyelinating polyneuropathy

Respiratory, Thoracic and Mediastinal Disorders: Acute diffuse infiltrative pulmonary disease

Skin and Subcutaneous Tissue Disorders: Stevens-Johnson syndrome/toxic epidermal necrolysis (SJS/TEN), acute febrile neutrophilic dermatosis (Sweet's syndrome)

7 DRUG INTERACTIONS

7.1 Effects of Other Drugs on Bortezomib

Strong CYP3A4 Inducers

Coadministration with a strong CYP3A4 inducer decreases the exposure of bortezomib [see Clinical Pharmacology (12.3)] which may decrease Bortezomib for Injection efficacy. Avoid coadministration with strong CYP3A4 inducers.

Strong CYP3A4 Inhibitors

Coadministration with a strong CYP3A4 inhibitor increases the exposure of bortezomib [see Clinical Pharmacology (12.3)] which may increase the risk of Bortezomib for Injection toxicities. Monitor patients for signs of bortezomib toxicity and consider a bortezomib dose reduction if bortezomib must be given in combination with strong CYP3A4 inhibitors.

7.2 Drugs Without Clinically Significant Interactions with Bortezomib

No clinically significant drug interactions have been observed when Bortezomib for Injection was coadministered with dexamethasone, omeprazole, or melphalan in combination with prednisone [see Clinical Pharmacology (12.3)].

8 USE IN SPECIFIC POPULATIONS

8.1 Pregnancy

Risk Summary

Based on its mechanism of action [see Clinical Pharmacology (12.1)] and findings in animals, Bortezomib for Injection can cause fetal harm when administered to a pregnant woman. There are no studies with the use of bortezomib in pregnant women to inform drug-associated risks. Bortezomib caused embryo-fetal lethality in rabbits at doses lower than the clinical dose (see Data). Advise pregnant women of the potential risk to the fetus.

Adverse outcomes in pregnancy occur regardless of the health of the mother or the use of medications. The estimated background risk of major birth defects and miscarriage for the indicated population is unknown. In the U.S. general population, the estimated background risk of major birth defects and miscarriage in clinically recognized pregnancies is 2% to 4% and 15% to 20%, respectively.

Data

Animal Data

Bortezomib was not teratogenic in nonclinical developmental toxicity studies in rats and rabbits at the highest dose tested (0.075 mg/kg; 0.5 mg/m^2 in the rat and 0.05 mg/kg; 0.6 mg/m^2 in the rabbit) when administered during organogenesis. These dosages are approximately 0.5 times the clinical dose of 1.3 mg/m^2 based on body surface area.

Bortezomib caused embryo-fetal lethality in rabbits at doses lower than the clinical dose (approximately 0.5 times the clinical dose of 1.3 mg/m^2 based on body surface area). Pregnant rabbits given bortezomib during organogenesis at a dose of 0.05 mg/kg (0.6 mg/m^2) experienced significant post-implantation loss and decreased number of live fetuses. Live fetuses from these litters also showed significant decreases in fetal weight.

8.2 Lactation

Risk Summary

There are no data on the presence of bortezomib or its metabolites in human milk, the effects of the drug on the breastfed child, or the effects of the drug on milk production. Because many drugs are excreted in human milk and because the potential for serious adverse reactions in a breastfed child from bortezomib is unknown, advise nursing women not to breastfeed during treatment with Bortezomib for Injection and for two months after treatment.

8.3 Females and Males of Reproductive Potential

Based on its mechanism of action and findings in animals, Bortezomib for Injection can cause fetal harm when administered to a pregnant woman [see Use in Specific Populations (8.1)].

Pregnancy Testing

Conduct pregnancy testing in females of reproductive potential prior to initiating Bortezomib for Injection treatment.

Contraception

Females

Advise females of reproductive potential to use effective contraception during treatment with Bortezomib for Injection and for seven months after the last dose.

Males

Males with female partners of reproductive potential should use effective contraception during treatment with Bortezomib for Injection and for four months after the last dose.

Infertility

Based on the mechanism of action and findings in animals, Bortezomib for Injection may have an effect on either male or female fertility [see Nonclinical Toxicology (13.1)].

8.4 Pediatric Use

Safety and effectiveness have not been established in pediatric patients.

The activity and safety of bortezomib in combination with intensive reinduction chemotherapy was evaluated in pediatric and young adult patients with lymphoid malignancies (pre-B cell ALL 77%, 16% with T-cell ALL, and 7% T-cell lymphoblastic lymphoma (LL)), all of whom relapsed within 36 months of initial diagnosis in a single-arm multicenter, nonrandomized cooperative group trial. An effective reinduction multiagent chemotherapy regimen was administered in three blocks. Block 1 included vincristine, prednisone, doxorubicin and pegaspargase; Block 2 included cyclophosphamide, etoposide and methotrexate; Block 3 included high-dose cytosine arabinoside and asparaginase. Bortezomib was administered at a dose of 1.3 mg/m^2 as a bolus intravenous injection on Days 1, 4, 8, and 11 of Block 1 and Days 1, 4, and 8 of Block 2. There were 140 patients with ALL or LL enrolled and evaluated for safety. The median age was ten years (range: 1 to 26), 57% were male, 70% were white, 14% were black, 4% were Asian, 2% were American Indian/Alaska Native, 1% were Pacific Islander.

The activity was evaluated in a prespecified subset of the first 60 evaluable patients enrolled on the study with pre-B ALL ≤21 years and relapsed <36 months from diagnosis. The complete remission (CR) rate at Day 36 was compared to that in a historical control set of patients who had received the identical backbone therapy without bortezomib. There was no evidence that the addition of bortezomib had any impact on the CR rate.

No new safety concerns were observed when bortezomib was added to a chemotherapy backbone regimen as compared with a historical control group in which the backbone regimen was given without bortezomib.

The BSA-normalized clearance of bortezomib in pediatric patients was similar to that observed in adults.

8.5 Geriatric Use

Of the 669 patients enrolled in the relapsed multiple myeloma study, 245 (37%) were 65 years of age or older: 125 (38%) on the bortezomib arm and 120 (36%) on the dexamethasone arm. Median time to progression and median duration of response for patients ≥65 were longer on bortezomib compared to dexamethasone [5.5 mo vs 4.3 mo, and 8.0 mo vs 4.9 mo, respectively]. On the bortezomib arm, 40% (n=46) of evaluable patients aged ≥65 experienced response (CR + PR) vs 18% (n=21) on the dexamethasone arm. The incidence of Grade 3 and 4 events was 64%, 78% and 75% for bortezomib patients ≤50, 51 to 64 and ≥65 years old, respectively [see Adverse Reactions (6.1), Clinical Studies (14.1)].

No overall differences in safety or effectiveness were observed between patients ≥age 65 and younger patients receiving bortezomib; but greater sensitivity of some older individuals cannot be ruled out.

8.6 Renal Impairment

No starting dosage adjustment of Bortezomib for Injection is recommended for patients with renal impairment. In patients requiring dialysis, Bortezomib for Injection should be administered after the dialysis procedure [see Clinical Pharmacology (12.3)].

8.7 Hepatic Impairment

No starting dosage adjustment of Bortezomib for Injection is recommended for patients with mild hepatic impairment (total bilirubin ≤1× ULN and AST >ULN, or total bilirubin >1 to 1.5× ULN and any AST). The exposure of bortezomib is increased in patients with moderate (total bilirubin ≥1.5 to 3× ULN and any AST) and severe (total bilirubin >3× ULN and any AST) hepatic impairment. Reduce the starting dose in patients with moderate or severe hepatic impairment [see Dosage and Administration (2.8), Clinical Pharmacology (12.3)].

8.8 Patients with Diabetes

During clinical trials, hypoglycemia and hyperglycemia were reported in diabetic patients receiving oral hypoglycemics. Patients on oral antidiabetic agents receiving Bortezomib for Injection treatment may require close monitoring of their blood glucose levels and adjustment of the dose of their antidiabetic medication.

10 OVERDOSAGE

There is no known specific antidote for Bortezomib for Injection overdosage. In humans, fatal outcomes following the administration of more than twice the recommended therapeutic dose have been reported, which were associated with the acute onset of symptomatic hypotension (5.2) and thrombocytopenia (5.7). In the event of an overdosage, the patient's vital signs should be monitored and appropriate supportive care given.

Studies in monkeys and dogs showed that intravenous bortezomib doses as low as two times the recommended clinical dose on a mg/m^2 basis were associated with increases in heart rate, decreases in contractility, hypotension, and death. In dog studies, a slight increase in the corrected QT interval was observed at doses resulting in death. In monkeys, doses of 3 mg/m^2 and greater (approximately twice the recommended clinical dose) resulted in hypotension starting at one hour post-administration, with progression to death in 12 to 14 hours following drug administration.

11 DESCRIPTION

Bortezomib for Injection, a proteasome inhibitor, is an antineoplastic agent. Bortezomib is a modified dipeptidyl boronic acid. The chemical name for bortezomib, the monomeric boronic acid, is [(1R)-3-methyl-1-[[(2S)-1-oxo-3-phenyl-2[(pyrazinylcarbonyl) amino]propyl]amino]butyl] boronic acid.

Bortezomib has the following chemical structure:

The molecular weight is 384.24 g/mol. The molecular formula is C19H25BN4O4. The solubility of bortezomib, as the monomeric boronic acid, in water is 3.3 to 3.8 mg/mL in a pH range of 2 to 6.5.

Bortezomib for Injection is available for intravenous injection or subcutaneous use. Each single-dose vial contains 1 mg or 2.5 mg of bortezomib as a sterile lyophilized powder. It also contains the inactive ingredient: 10 mg or 25 mg mannitol, USP for the 1 mg and 2.5 mg single-dose vial, respectively. The product is provided as a mannitol boronic ester which, in reconstituted form, consists of the mannitol ester in equilibrium with its hydrolysis product, the monomeric boronic acid. The drug substance exists in its monohydrate form.

12 CLINICAL PHARMACOLOGY

12.1 Mechanism of Action

Bortezomib is a reversible inhibitor of the chymotrypsin-like activity of the 26S proteasome in mammalian cells. The 26S proteasome is a large protein complex that degrades ubiquitinated proteins. The ubiquitin-proteasome pathway plays an essential role in regulating the intracellular concentration of specific proteins, thereby maintaining homeostasis within cells. Inhibition of the 26S proteasome prevents this targeted proteolysis, which can affect multiple signaling cascades within the cell. This disruption of normal homeostatic mechanisms can lead to cell death. Experiments have demonstrated that bortezomib is cytotoxic to a variety of cancer cell types in vitro. Bortezomib causes a delay in tumor growth in vivo in nonclinical tumor models, including multiple myeloma.

12.2 Pharmacodynamics

Following twice weekly administration of 1 mg/m^2 and 1.3 mg/m^2 bortezomib doses, the maximum inhibition of 20S proteasome activity (relative to baseline) in whole blood was observed five minutes after drug administration. Comparable maximum inhibition of 20S proteasome activity was observed between 1 mg/m^2 and 1.3 mg/m^2 doses. Maximal inhibition ranged from 70% to 84% and from 73% to 83% for the 1 mg/m^2 and 1.3 mg/m^2 dose regimens, respectively.

12.3 Pharmacokinetics

Following intravenous administration of 1 mg/m^2 and 1.3 mg/m^2 doses, the mean maximum plasma concentrations of bortezomib (Cmax) after the first dose (Day 1) were 57 ng/mL and 112 ng/mL, respectively. When administered twice weekly, the mean maximum observed plasma concentrations ranged from 67 ng/mL to 106 ng/mL for the 1 mg/m^2 dose and 89 ng/mL to 120 ng/mL for the 1.3 mg/m^2 dose.

Following an intravenous bolus or subcutaneous injection of a 1.3 mg/m^2 dose to patients with multiple myeloma, the total systemic exposure after repeat dose administration (AUClast) was equivalent for subcutaneous and intravenous administration. The AUClast geometric mean ratio (90% confidence interval) was 0.99 (0.80 to 1.23). The Cmax after subcutaneous administration (20.4 ng/mL) was lower than after intravenous administration (223 ng/mL) with repeat dose administration.

Distribution

The mean distribution volume of bortezomib ranged from approximately 498 L/m^2 to 1884 L/m^2 following single- or repeat-dose administration of 1 mg/m^2 or 1.3 mg/m^2 to patients with multiple myeloma. The binding of bortezomib to human plasma proteins averaged 83% over the concentration range of 100 ng/mL to 1000 ng/mL.

Elimination

The mean elimination half-life of bortezomib upon multiple dosing ranged from 40 hours to 193 hours after the 1 mg/m^2 dose and 76 hours to 108 hours after the 1.3 mg/m^2 dose. The mean total body clearance were 102 L/h and 112 L/h following the first dose for doses of 1 mg/m^2 and 1.3 mg/m^2, respectively, and ranged from 15 L/h to 32 L/h following subsequent doses for doses of 1 mg/m^2 and 1.3 mg/m^2, respectively.

Metabolism

Bortezomib is primarily oxidatively metabolized to several inactive metabolites in vitro via cytochrome P450 (CYP) enzymes 3A4, CYP2C19, and CYP1A2, and to a lesser extent by CYP2D6 and CYP2C9.

Excretion

The pathways of elimination of bortezomib have not been characterized in humans.

Specific Populations

No clinically significant differences in the pharmacokinetics of bortezomib were observed based on age, sex, or renal impairment (including patients administered bortezomib after dialysis). The effect of race on bortezomib pharmacokinetics is unknown.

Patients with Hepatic Impairment

Following administration of bortezomib doses ranging from 0.5 mg/m^2 to 1.3 mg/m^2, mild (total bilirubin ≤1× ULN and AST >ULN, or total bilirubin >1× to 1.5× ULN and any AST) hepatic impairment did not alter dose-normalized bortezomib AUC when compared to patients with normal hepatic function. Dose-normalized mean bortezomib AUC increased by approximately 60% in patients with moderate (total bilirubin >1.5× to 3× ULN and any AST) or severe (total bilirubin >3× ULN and any AST) hepatic impairment. A lower starting dose is recommended in patients with moderate or severe hepatic impairment.

Drug Interaction Studies

Clinical Studies

No clinically significant differences in bortezomib pharmacokinetics were observed when coadministered with dexamethasone (weak CYP3A4 inducer), omeprazole (strong CYP2C19 inhibitor), or melphalan in combination with prednisone.

Strong CYP3A4 Inhibitor

Coadministration with ketoconazole (strong CYP3A4 inhibitor) increased bortezomib exposure by 35%.

Strong CYP3A4 Inducer

Coadministration with rifampin (strong CYP3A4 inducer) decreased bortezomib exposure by approximately 45%.

In Vitro Studies

Bortezomib may inhibit CYP2C19 activity and increase exposure to drugs that are substrates for this enzyme.

13 NONCLINICAL TOXICOLOGY

13.1 Carcinogenesis, Mutagenesis, Impairment of Fertility

Carcinogenicity studies have not been conducted with bortezomib.

Bortezomib showed clastogenic activity (structural chromosomal aberrations) in the in vitro chromosomal aberration assay using Chinese hamster ovary cells. Bortezomib was not genotoxic when tested in the in vitro mutagenicity assay (Ames test) and in vivo micronucleus assay in mice.

Fertility studies with bortezomib were not performed but evaluation of reproductive tissues has been performed in the general toxicity studies. In the six-month rat toxicity study, degenerative effects in the ovary were observed at doses ≥0.3 mg/m^2 (one-fourth of the recommended clinical dose), and degenerative changes in the testes occurred at 1.2 mg/m^2.

13.2 Animal Toxicology and/or Pharmacology

Cardiovascular Toxicity

Studies in monkeys showed that administration of dosages approximately twice the recommended clinical dose resulted in heart rate elevations, followed by profound progressive hypotension, bradycardia, and death 12 to 14 hours postdose. Doses ≥1.2 mg/m^2 induced dose-proportional changes in cardiac parameters. Bortezomib has been shown to distribute to most tissues in the body, including the myocardium. In a repeated dosing toxicity study in the monkey, myocardial hemorrhage, inflammation, and necrosis were also observed.

Chronic Administration

In animal studies at a dose and schedule similar to that recommended for patients (twice weekly dosing for two weeks followed by one-week rest), toxicities observed included severe anemia and thrombocytopenia, and gastrointestinal, neurological and lymphoid system toxicities. Neurotoxic effects of bortezomib in animal studies included axonal swelling and degeneration in peripheral nerves, dorsal spinal roots, and tracts of the spinal cord. Additionally, multifocal hemorrhage and necrosis in the brain, eye, and heart were observed.

14 CLINICAL STUDIES

14.1 Multiple Myeloma

Randomized, Open-Label Clinical Study in Patients with Previously Untreated Multiple Myeloma

A prospective, international, randomized (1:1), open-label clinical study (NCT00111319) of 682 patients was conducted to determine whether bortezomib administered intravenously (1.3 mg/m^2) in combination with melphalan (9 mg/m^2) and prednisone (60 mg/m^2) resulted in improvement in time to progression (TTP) when compared to melphalan (9 mg/m^2) and prednisone (60 mg/m^2) in patients with previously untreated multiple myeloma. Treatment was administered for a maximum of nine cycles (approximately 54 weeks) and was discontinued early for disease progression or unacceptable toxicity. Antiviral prophylaxis was recommended for patients on the bortezomib study arm.

The median age of the patients in the study was 71 years (48;91), 50% were male, 88% were Caucasian and the median Karnofsky performance status score for the patients was 80 (60;100). Patients had IgG/IgA/Light chain myeloma in 63%/25%/8% instances, a median hemoglobin of 105 g/L (64;165), and a median platelet count of 221,500/microliter (33,000;587,000).

Efficacy results for the trial are presented in Table 14. At a pre-specified interim analysis (with median follow-up of 16.3 months), the combination of bortezomib, melphalan and prednisone therapy resulted in significantly superior results for time to progression, progression-free survival, overall survival and response rate. Further enrollment was halted, and patients receiving melphalan and prednisone were offered bortezomib in addition. A later, pre-specified analysis of overall survival (with median follow-up of 36.7 months with a hazard ratio of 0.65, 95% CI: 0.51, 0.84) resulted in a statistically significant survival benefit for the bortezomib, melphalan and prednisone treatment arm despite subsequent therapies including bortezomib based regimens. In an updated analysis of overall survival based on 387 deaths (median follow-up 60.1 months), the median overall survival for the bortezomib, melphalan and prednisone treatment arm was 56.4 months and for the melphalan and prednisone treatment arm was 43.1 months, with a hazard ratio of 0.695 (95% CI: 0.57, 0.85).

Table 14: Summary of Efficacy Analyses in the Previously Untreated Multiple Myeloma Study
Efficacy Endpoint | Bortezomib, Melphalan and Prednisone (n=344) | Melphalan and Prednisone (n=338)
Time to Progression
Events n (%) | 101 (29) | 152 (45)
Median [Kaplan-Meier estimate] (months) | 20.7 | 15.0
(95% CI) | (17.6, 24.7) | (14.1, 17.9)
Hazard ratio [Hazard ratio estimate is based on a Cox proportional-hazard model adjusted for stratification factors: beta2-microglobulin, albumin, and region. A hazard ratio less than one indicates an advantage for bortezomib, melphalan and prednisone] | 0.54
(95% CI) | (0.42, 0.70)
p-value [p-value based on the stratified log-rank test adjusted for stratification factors: beta2-microglobulin, albumin, and region] | 0.000002
Progression-Free Survival
Events n (%) | 135 (39) | 190 (56)
Median (months) | 18.3 | 14.0
(95% CI) | (16.6, 21.7) | (11.1, 15.0)
Hazard ratio | 0.61
(95% CI) | (0.49, 0.76)
p-value | 0.00001
Response Rate
CR [EBMT criteria] n (%) | 102 (30) | 12 (4)
PR n (%) | 136 (40) | 103 (30)
nCR n (%) | 5 (1) | 0
CR + PR n (%) | 238 (69) | 115 (34)
p-value [p-value for Response Rate (CR + PR) from the Cochran-Mantel-Haenszel chi-square test adjusted for the stratification factors] | <10^-10
Overall Survival at Median Follow-Up of 36.7 Months
Events (deaths) n (%) | 109 (32) | 148 (44)
Median (months) | Not Reached | 43.1
(95% CI) | (46.2, NR) | (34.8, NR)
Hazard ratio | 0.65
(95% CI) | (0.51, 0.84)
p-value | 0.00084
Note: All results are based on the analysis performed at a median follow-up duration of 16.3 months except for the overall survival analysis.

TTP was statistically significantly longer on the bortezomib, melphalan and prednisone arm (see Figure 1) (median follow-up 16.3 months).

Figure 1: Time to Progression Bortezomib, Melphalan, and Prednisone versus Melphalan and Prednisone

Overall survival was statistically significantly longer on the bortezomib, melphalan and prednisone arm (see Figure 2) (median follow-up 60.1 months).

Figure 2: Overall Survival Bortezomib, Melphalan and Prednisone versus Melphalan and Prednisone

Randomized, Clinical Study in Relapsed Multiple Myeloma of Bortezomib vs Dexamethasone

A prospective Phase 3, international, randomized (1:1), stratified, open-label clinical study (NCT00048230) enrolling 669 patients was designed to determine whether bortezomib resulted in improvement in time to progression (TTP) compared to high-dose dexamethasone in patients with progressive multiple myeloma following 1 to 3 prior therapies. Patients considered to be refractory to prior high-dose dexamethasone were excluded as were those with baseline Grade ≥2 peripheral neuropathy or platelet counts <50,000/μL. A total of 627 patients were evaluable for response.

Stratification factors were based on the number of lines of prior therapy the patient had previously received (one previous line vs more than one line of therapy), time of progression relative to prior treatment (progression during or within six months of stopping their most recent therapy vs relapse >6 months after receiving their most recent therapy), and screening beta2-microglobulin levels (≤2.5 mg/L vs >2.5 mg/L).

Baseline patient and disease characteristics are summarized in Table 15.

Table 15: Summary of Baseline Patient and Disease Characteristics in the Relapsed Multiple Myeloma Study
Patient Characteristics | Bortezomib (N=333) | Dexamethasone (N=336)
Median age in years (range) | 62.0 (33, 84) | 61.0 (27, 86)
Gender: Male/female | 56% / 44% | 60% / 40%
Race: Caucasian/black/other | 90% / 6% / 4% | 88% / 7% / 5%
Karnofsky performance status score ≤70 | 13% | 17%
Hemoglobin <100 g/L | 32% | 28%
Platelet count <75 × 10^9/L | 6% | 4%
Disease Characteristics
Type of myeloma (%): IgG/IgA/Light chain | 60% / 23% / 12% | 59% / 24% / 13%
Median beta2-microglobulin (mg/L) | 3.7 | 3.6
Median albumin (g/L) | 39.0 | 39.0
Creatinine clearance ≤30 mL/min [n (%)] | 17 (5%) | 11 (3%)
Median Duration of Multiple Myeloma Since Diagnosis (Years) | 3.5 | 3.1
Number of Prior Therapeutic Lines of Treatment
Median | 2 | 2
1 prior line | 40% | 35%
>1 prior line | 60% | 65%
Previous Therapy
Any prior steroids, e.g., dexamethasone, VAD | 98% | 99%
Any prior anthracyclines, e.g., VAD, mitoxantrone | 77% | 76%
Any prior alkylating agents, e.g., MP, VBMCP | 91% | 92%
Any prior thalidomide therapy | 48% | 50%
Vinca alkaloids | 74% | 72%
Prior stem cell transplant/other high-dose therapy | 67% | 68%
Prior experimental or other types of therapy | 3% | 2%

Patients in the bortezomib treatment group were to receive 8, three week treatment cycles followed by 3, five week treatment cycles of bortezomib. Patients achieving a CR were treated for four cycles beyond first evidence of CR. Within each three week treatment cycle, bortezomib 1.3 mg/m^2/dose alone was administered by intravenous bolus twice weekly for two weeks on Days 1, 4, 8, and 11 followed by a ten day rest period (Days 12 to 21). Within each five week treatment cycle, bortezomib 1.3 mg/m^2/dose alone was administered by intravenous bolus once weekly for four weeks on Days 1, 8, 15, and 22 followed by a 13 day rest period (Days 23 to 35) [see Dosage and Administration (2.2)].

Patients in the dexamethasone treatment group were to receive 4, five week treatment cycles followed by 5, four week treatment cycles. Within each five week treatment cycle, dexamethasone 40 mg/day PO was administered once daily on Days 1 to 4, 9 to 12, and 17 to 20 followed by a 15 day rest period (Days 21 to 35). Within each four week treatment cycle, dexamethasone 40 mg/day PO was administered once daily on Days 1 to 4 followed by a 24 day rest period (Days 5 to 28). Patients with documented progressive disease on dexamethasone were offered bortezomib at a standard dose and schedule on a companion study. Following a preplanned interim analysis of time to progression, the dexamethasone arm was halted and all patients randomized to dexamethasone were offered bortezomib, regardless of disease status.

In the bortezomib arm, 34% of patients received at least one bortezomib dose in all eight of the three week cycles of therapy, and 13% received at least one dose in all 11 cycles. The average number of bortezomib doses during the study was 22, with a range of 1 to 44. In the dexamethasone arm, 40% of patients received at least one dose in all four of the five week treatment cycles of therapy, and 6% received at least one dose in all nine cycles.

The time to event analyses and response rates from the relapsed multiple myeloma study are presented in Table 16. Response and progression were assessed using the European Group for Blood and Marrow Transplantation (EBMT) criteria. Complete response (CR) required <5% plasma cells in the marrow, 100% reduction in M-protein, and a negative immunofixation test (IF^-). Partial response (PR) requires ≥50% reduction in serum myeloma protein and ≥90% reduction of urine myeloma protein on at least two occasions for a minimum of at least six weeks along with stable bone disease and normal calcium. Near complete response (nCR) was defined as meeting all the criteria for complete response including 100% reduction in M-protein by protein electrophoresis; however, M-protein was still detectable by immunofixation (IF^+).

Table 16: Summary of Efficacy Analyses in the Relapsed Multiple Myeloma Study
 | All Patients |  | 1 Prior Line of Therapy |  | >1 Prior Line of Therapy
 | Bortezomib | Dex | Bortezomib | Dex | Bortezomib | Dex
Efficacy Endpoint | (n=333) | (n=336) | (n=132) | (n=119) | (n=200) | n=217
Time to Progression
Events n (%) | 147 (44) | 196 (58) | 55 (42) | 64 (54) | 92 (46) | 132 (61)
Median [Kaplan-Meier estimate] (95% CI) | 6.2 mo (4.9, 6.9) | 3.5 mo (2.9, 4.2) | 7.0 mo (6.2, 8.8) | 5.6 mo (3.4, 6.3) | 4.9 mo (4.2, 6.3) | 2.9 mo (2.8, 3.5)
Hazard ratio [Hazard ratio is based on Cox proportional-hazard model with the treatment as single independent variable. A hazard ratio less than one indicates an advantage for bortezomib] (95% CI) | 0.55 (0.44, 0.69) |  | 0.55 (0.38, 0.81) |  | 0.54 (0.41, 0.72)
p-value [p-value based on the stratified log-rank test including randomization stratification factors] | <0.0001 |  | 0.0019 |  | <0.0001
Overall Survival
Events (deaths) n (%) | 51 (15) | 84 (25) | 12 (9) | 24 (20) | 39 (20) | 60 (28)
Hazard ratio (95% CI) | 0.57 (0.40, 0.81) |  | 0.39 (0.19, 0.81) |  | 0.65 (0.43, 0.97)
p-value , [Precise p-value cannot be rendered] | <0.05 |  | <0.05 |  | <0.05
Response Rate
Population [Response population includes patients who had measurable disease at baseline and received at least one dose of study drug] n=627 | n=315 | n=312 | n=128 | n=110 | n=187 | n=202
CR [EBMT criteria; nCR meets all EBMT criteria for CR but has positive IF. Under EBMT criteria nCR is in the PR category] n (%) | 20 (6) | 2 (<1) | 8 (6) | 2 (2) | 12 (6) | 0 (0)
PR n (%) | 101 (32) | 54 (17) | 49 (38) | 27 (25) | 52 (28) | 27 (13)
nCR , [In two patients, the IF was unknown] n (%) | 21 (7) | 3 (<1) | 8 (6) | 2 (2) | 13 (7) | 1 (<1)
CR + PR n (%) | 121 (38) | 56 (18) | 57 (45) | 29 (26) | 64 (34) | 27 (13)
p-value [p-value for Response Rate (CR + PR) from the Cochran-Mantel-Haenszel chi-square test adjusted for the stratification factors] | <0.0001 |  | 0.0035 |  | <0.0001

TTP was statistically significantly longer on the bortezomib arm (see Figure 3).

Figure 3: Time to Progression Bortezomib vs Dexamethasone (Relapsed Multiple Myeloma Study)

As shown in Figure 4, bortezomib had a significant survival advantage relative to dexamethasone (p < 0.05). The median follow-up was 8.3 months.

Figure 4: Overall Survival Bortezomib vs Dexamethasone (Relapsed Multiple Myeloma Study)

For the 121 patients achieving a response (CR or PR) on the bortezomib arm, the median duration was 8.0 months (95% CI: 6.9, 11.5 months) compared to 5.6 months (95% CI: 4.8, 9.2 months) for the 56 responders on the dexamethasone arm. The response rate was significantly higher on the bortezomib arm regardless of beta2-microglobulin levels at baseline.

Randomized, Open-Label Clinical Study of Bortezomib Subcutaneous vs Intravenous in Relapsed Multiple Myeloma

An open-label, randomized, Phase 3 non-inferiority study (NCT00722566) compared the efficacy and safety of the subcutaneous administration of bortezomib vs the intravenous administration. This study included 222 bortezomib naïve patients with relapsed multiple myeloma, who were randomized in a 2:1 ratio to receive 1.3 mg/m^2 of bortezomib by either the subcutaneous (n=148) or intravenous (n=74) route for eight cycles. Patients who did not obtain an optimal response (less than Complete Response (CR)) to therapy with bortezomib alone after four cycles were allowed to receive oral dexamethasone 20 mg daily on the day of and after bortezomib administration (82 patients in subcutaneous treatment group and 39 patients in the intravenous treatment group). Patients with baseline Grade ≥2 peripheral neuropathy or neuropathic pain, or platelet counts <50,000/μL were excluded. A total of 218 patients were evaluable for response.

Stratification factors were based on the number of lines of prior therapy the patient had received (one previous line vs more than one line of therapy), and international staging system (ISS) stage (incorporating beta2-microglobulin and albumin levels; Stages I, II, or III).

The baseline demographic and other characteristics of the two treatment groups are summarized as follows: the median age of the patient population was approximately 64 years of age (range: 38 to 88 years), primarily male (subcutaneous: 50%, intravenous: 64%); the primary type of myeloma is IgG (subcutaneous: 65% IgG, 26% IgA, 8% light chain; intravenous: 72% IgG, 19% IgA, 8% light chain), ISS staging I/II/III (%) was 27, 41, 32 for both subcutaneous and intravenous, Karnofsky performance status score was ≤70% in 22% of subcutaneous and 16% of intravenous, creatinine clearance was 67.5 mL/min in subcutaneous and 73 mL/min in intravenous, the median years from diagnosis was 2.68 and 2.93 in subcutaneous and intravenous respectively and the proportion of patients with more than one prior line of therapy was 38% in subcutaneous and 35% in intravenous.

This study met its primary (non-inferiority) objective that single agent subcutaneous bortezomib retains at least 60% of the overall response rate after four cycles relative to single agent intravenous bortezomib. The results are provided in Table 17.

Table 17: Summary of Efficacy Analyses in the Relapsed Multiple Myeloma Study of Bortezomib Subcutaneous vs Intravenous
 | Subcutaneous Bortezomib | Intravenous Bortezomib
Intent to Treat Population | (n=148) | (n=74)
Primary Endpoint
Response Rate at 4 Cycles
ORR (CR + PR) n (%) | 63 (43) | 31 (42)
Ratio of Response Rates (95% CI) | 1.01 (0.73, 1.40)
CR n (%) | 11 (7) | 6 (8)
PR n (%) | 52 (35) | 25 (34)
nCR n (%) | 9 (6) | 4 (5)
Secondary Endpoints
Response Rate at 8 Cycles
ORR (CR + PR) | 78 (53) | 38 (51)
CR n (%) | 17 (11) | 9 (12)
PR n (%) | 61 (41) | 29 (39)
nCR n (%) | 14 (9) | 7 (9)
Median Time to Progression, months | 10.4 | 9.4
Median Progression-Free Survival, months | 10.2 | 8.0
1-Year Overall Survival (%) [Median duration of follow-up is 11.8 months] | 72.6 | 76.7

A Randomized, Phase 2 Dose-Response Study in Relapsed Multiple Myeloma

An open-label, multicenter study randomized 54 patients with multiple myeloma who had progressed or relapsed on or after front-line therapy to receive bortezomib 1 mg/m^2 or 1.3 mg/m^2 intravenous bolus twice weekly for two weeks on Days 1, 4, 8, and 11 followed by a ten day rest period (Days 12 to 21). The median duration of time between diagnosis of multiple myeloma and first dose of bortezomib on this trial was two years, and patients had received a median of one prior line of treatment (median of three prior therapies). A single complete response was seen at each dose. The overall response rates (CR + PR) were 30% (8/27) at 1 mg/m^2 and 38% (10/26) at 1.3 mg/m^2.

A Phase 2 Open-Label Extension Study in Relapsed Multiple Myeloma

Patients from the two Phase 2 studies, who in the investigators' opinion would experience additional clinical benefit, continued to receive bortezomib beyond 8 cycles on an extension study. Sixty-three (63) patients from the Phase 2 multiple myeloma studies were enrolled and received a median of seven additional cycles of bortezomib therapy for a total median of 14 cycles (range: 7 to 32). The overall median dosing intensity was the same in both the parent protocol and extension study. Sixty-seven percent (67%) of patients initiated the extension study at the same or higher dose intensity at which they completed the parent protocol, and 89% of patients maintained the standard three week dosing schedule during the extension study. No new cumulative or new long-term toxicities were observed with prolonged bortezomib treatment [see Adverse Reactions (6.1)].

A Single-Arm Trial of Retreatment in Relapsed Multiple Myeloma

A single-arm, open-label trial (NCT00431769) was conducted to determine the efficacy and safety of retreatment with bortezomib. One hundred and thirty patients (≥18 years of age) with multiple myeloma who previously had at least partial response on a bortezomib-containing regimen (median of two prior lines of therapy [range: 1 to 7]) were retreated upon progression with bortezomib administered intravenously. Patients were excluded from trial participation if they had peripheral neuropathy or neuropathic pain of Grade ≥2. At least six months after prior bortezomib therapy, bortezomib was restarted at the last tolerated dose of 1.3 mg/m^2 (n=93) or ≤1 mg/m^2 (n=37) and given on Days 1, 4, 8 and 11 every three weeks for maximum of eight cycles either as single agent or in combination with dexamethasone in accordance with the standard of care. Dexamethasone was administered in combination with bortezomib to 83 patients in Cycle 1 with an additional 11 patients receiving dexamethasone during the course of bortezomib retreatment cycles.

The primary endpoint was best confirmed response to retreatment as assessed by European Group for Blood and Marrow Transplantation (EBMT) criteria. Fifty of the 130 patients achieved a best confirmed response of Partial Response or better for an overall response rate of 38.5% (95% CI: 30.1, 47.4). One patient achieved a Complete Response and 49 achieved Partial Response. In the 50 responding patients, the median duration of response was 6.5 months and the range was 0.6 to 19.3 months.

14.2 Mantle Cell Lymphoma

A Randomized, Open-Label Clinical Study in Patients with Previously Untreated Mantle Cell Lymphoma

A randomized, open-label, Phase 3 study (NCT00722137) was conducted in 487 adult patients with previously untreated mantle cell lymphoma (Stage II, III or IV) who were ineligible or not considered for bone marrow transplantation to determine whether bortezomib administered in combination with rituximab, cyclophosphamide, doxorubicin, and prednisone (VcR-CAP) resulted in improvement in progression-free survival (PFS) when compared to the combination of rituximab, cyclophosphamide, doxorubicin, vincristine, and prednisone (R-CHOP). This clinical study utilized independent pathology confirmation and independent radiologic response assessment.

Patients in the VcR-CAP treatment arm received bortezomib (1.3 mg/m^2) administered intravenously on Days 1, 4, 8, and 11 (rest period Days 12 to 21); rituximab (375 mg/m^2) on Day 1; cyclophosphamide (750 mg/m^2) on Day 1; doxorubicin (50 mg/m^2) on Day 1; and prednisone (100 mg/m^2) on Day 1 through Day 5 of the 21 day treatment cycle. For patients with a response first documented at Cycle 6, two additional treatment cycles were allowed.

Median patient age was 66 years, 74% were male, 66% were Caucasian and 32% were Asian. Sixty-nine percent of patients had a positive bone marrow aspirate and/or a positive bone marrow biopsy for MCL, 54% of patients had an International Prognostic Index (IPI) score of three (high-intermediate) or higher and 76% had Stage IV disease.

The majority of the patients in both groups received six or more cycles of treatment, 84% in the VcR-CAP group and 83% in the R-CHOP group. Median number of cycles received by patients in both treatment arms was six with 17% of patients in the R-CHOP group and 14% of subjects in the VcR-CAP group receiving up to two additional cycles.

The efficacy results for PFS, CR and ORR with a median follow-up of 40 months are presented in Table 18. The response criteria used to assess efficacy were based on the International Workshop to Standardize Response Criteria for Non-Hodgkin's Lymphoma (IWRC). Final overall survival results at a median follow-up of 78.5 months are also presented in Table 18 and Figure 6. The combination of VcR-CAP resulted in statistically significant prolongation of PFS compared with R-CHOP (see Table 18, Figure 5).

Table 18: Summary of Efficacy Analyses in the Previously Untreated Mantle Cell Lymphoma Study
Efficacy Endpoint n: Intent to Treat patients | VcR-CAP (n=243) | R-CHOP (n=244)
Progression-Free Survival (by independent radiographic assessment)
Events n (%) | 133 (55) | 165 (68)
Median [Based on Kaplan-Meier product limit estimates.] (months) | 25 | 14
(95% CI) | (20, 32) | (12, 17)
Hazard ratio [Hazard ratio estimate is based on a Cox's model stratified by IPI risk and stage of disease. A hazard ratio <1 indicates an advantage for VcR-CAP.] | 0.63
(95% CI) | (0.50, 0.79)
p-value [Based on Log-rank test stratified with IPI risk and stage of disease.] | <0.001
Complete Response Rate (CR) [Includes CR by independent radiographic assessment, bone marrow, and LDH using ITT population.]
n (%) | 108 (44) | 82 (34)
(95% CI) | (38, 51) | (28, 40)
Overall Response Rate (CR + CRu + PR) [Includes CR + CRu + PR by independent radiographic assessment, regardless of the verification by bone marrow and LDH, using ITT population.]
n (%) | 214 (88) | 208 (85)
(95% CI) | (83, 92) | (80, 89)
Overall Survival
Events n (%) | 103 (42) | 138 (57)
Median (months) | 91 | 56
(95% CI) | (71, NE) | (47, 69)
Hazard ratio | 0.66
(95% CI) | (0.51, 0.85)
Note: All results are based on the analysis performed at a median follow-up duration of 40 months except for the overall survival analysis, which was performed at a median follow-up of 78.5 months.
CI = Confidence Interval; IPI = International Prognostic Index; LDH = Lactate dehydrogenase

Figure 5: Progression-Free Survival VcR-CAP vs R-CHOP (previously Untreated Mantle Cell Lymphoma Study)

Key: R-CHOP = rituximab, cyclophosphamide, doxorubicin, vincristine, and prednisone; VcR-CAP = bortezomib, rituximab, cyclophosphamide, doxorubicin, and prednisone.

Figure 6: Overall Survival VcR-CAP vs R-CHOP (previously Untreated Mantle Cell Lymphoma Study)

Key: R-CHOP = rituximab, cyclophosphamide, doxorubicin, vincristine, and prednisone; VcR-CAP = bortezomib, rituximab, cyclophosphamide, doxorubicin, and prednisone.

A Phase 2 Single-Arm Clinical Study in Relapsed Mantle Cell Lymphoma after Prior Therapy

The safety and efficacy of bortezomib in relapsed or refractory mantle cell lymphoma were evaluated in an open-label, single-arm, multicenter study (NCT00063713) of 155 patients with progressive disease who had received at least one prior therapy. The median age of the patients was 65 years (42, 89), 81% were male, and 92% were Caucasian. Of the total, 75% had one or more extra-nodal sites of disease, and 77% were Stage 4. In 91% of the patients, prior therapy included all of the following: an anthracycline or mitoxantrone, cyclophosphamide, and rituximab. A total of thirty-seven percent (37%) of patients were refractory to their last prior therapy. An intravenous bolus injection of bortezomib 1.3 mg/m^2/dose was administered twice weekly for two weeks on Days 1, 4, 8, and 11 followed by a ten day rest period (Days 12 to 21) for a maximum of 17 treatment cycles. Patients achieving a CR or CRu were treated for four cycles beyond first evidence of CR or CRu. The study employed dose modifications for toxicity [see Dosage and Administration (2.6, 2.7)].

Responses to bortezomib are shown in Table 19. Response rates to bortezomib were determined according to the International Workshop Response Criteria (IWRC) based on independent radiologic review of CT scans. The median number of cycles administered across all patients was four; in responding patients the median number of cycles was eight. The median time to response was 40 days (range: 31 to 204 days). The median duration of follow-up was more than 13 months.

Table 19: Response Outcomes in a Phase 2 Relapsed Mantle Cell Lymphoma Study
Response Analyses (N=155) | N (%) | 95% CI
Overall Response Rate (IWRC) (CR + CRu + PR) | 48 (31) | (24, 39)
Complete Response (CR + CRu) | 12 (8) | (4, 13)
CR | 10 (6) | (3, 12)
CRu | 2 (1) | (0, 5)
Partial Response (PR) | 36 (23) | (17, 31)
Duration of Response | Median | 95% CI
CR + CRu + PR (N=48) | 9.3 months | (5.4, 13.8)
CR + CRu (N=12) | 15.4 months | (13.4, 15.4)
PR (N=36) | 6.1 months | (4.2, 9.3)

15 REFERENCES

1. "OSHA Hazardous Drugs" (refer to antineoplastic weblinks including OSHA Technical Manual). OSHA. http://www.osha.gov/SLTC/hazardousdrugs/index.html

16 HOW SUPPLIED/STORAGE AND HANDLING

Bortezomib for Injection is supplied as individually cartoned 5 mL or 10 mL vials containing 1 mg or 2.5 mg of bortezomib, respectively, as a white to off-white cake or powder.

Unit of Sale | Strength
NDC 0409-1704-01 1 Single-dose vial in a carton | 1 mg/vial
NDC 0409-1703-01 1 Single-dose vial in a carton | 2.5 mg/vial

STORAGE AND HANDLING

Unopened vials may be stored at controlled room temperature 20°C to 25°C (68°F to 77°F); excursions permitted from 15°C to 30°C (59°F to 86°F) [see USP Controlled Room Temperature]. Retain in original package to protect from light.

Follow guidelines for handling and disposal for hazardous drugs, including the use of gloves and other protective clothing to prevent skin contact^1.

17 PATIENT COUNSELING INFORMATION

Discuss the following with patients prior to treatment with Bortezomib for Injection:

Peripheral Neuropathy

Advise patients to report the development or worsening of sensory and motor peripheral neuropathy to their healthcare provider [see Warnings and Precautions (5.1)].

Hypotension

Advise patients to drink adequate fluids to avoid dehydration and to report symptoms of hypotension to their healthcare provider [see Warnings and Precautions (5.2)].

Instruct patients to seek medical advice if they experience symptoms of dizziness, light headedness or fainting spells, or muscle cramps.

Cardiac Toxicity

Advise patients to report signs or symptoms of heart failure to their healthcare provider [see Warnings and Precautions (5.3)].

Pulmonary Toxicity

Advise patients to report symptoms of ARDS, pulmonary hypertension, pneumonitis, and pneumonia immediately to their healthcare provider [see Warnings and Precautions (5.4)].

Posterior Reversible Encephalopathy Syndrome (PRES)

Advise patients to seek immediate medical attention for signs or symptoms of PRES [see Warnings and Precautions (5.5)].

Gastrointestinal Toxicity

Advise patients to report symptoms of gastrointestinal toxicity to their healthcare provider and to drink adequate fluids to avoid dehydration. Instruct patients to seek medical advice if they experience symptoms of dizziness, light headedness or fainting spells, or muscle cramps [see Warnings and Precautions (5.6)].

Thrombocytopenia/Neutropenia

Advise patients to report signs or symptoms of bleeding or infection immediately to their healthcare provider [see Warnings and Precautions (5.7)].

Tumor Lysis Syndrome

Advise patients of the risk of tumor lysis syndrome and to drink adequate fluids to avoid dehydration [see Warnings and Precautions (5.8)].

Hepatic Toxicity

Advise patients to report signs or symptoms of hepatic toxicity to their healthcare provider [see Warnings and Precautions (5.9)].

Thrombotic Microangiopathy

Advise patients to seek immediate medical attention if any signs or symptoms of thrombotic microangiopathy occur [see Warnings and Precautions (5.10)].

Ability to Drive or Operate Machinery or Impairment of Mental Ability

Bortezomib for Injection may cause fatigue, dizziness, syncope, orthostatic/postural hypotension. Advise patients not to drive or operate machinery if they experience any of these symptoms [see Warnings and Precautions (5.2, 5.5)].

Embryo-Fetal Toxicity

Advise females of the potential risk to the fetus and to use effective contraception during treatment with Bortezomib for Injection and for seven months following the last dose. Advise male patients with female partners of reproductive potential to use effective contraception during treatment with Bortezomib for Injection and for four months following the last dose. Instruct patients to report pregnancy to their physicians immediately if they or their female partner becomes pregnant during treatment or within seven months following last dose [see Warnings and Precautions (5.11)].

Lactation

Advise women not to breastfeed while receiving Bortezomib for Injection and for two months after last dose [see Use in Specific Populations (8.2)].

Concomitant Medications

Advise patients to speak with their physicians about any other medication they are currently taking.

Diabetic Patients

Advise patients to check their blood sugar frequently if using an oral antidiabetic medication and to notify their physicians of any changes in blood sugar level.

Dermal

Advise patients to contact their physicians if they experience rash, severe injection site reactions [see Dosage and Administration (2.9)], or skin pain. Discuss with patients the option for antiviral prophylaxis for herpes virus infection [see Adverse Reactions (6.1)].

Other

Instruct patients to contact their physicians if they develop an increase in blood pressure, bleeding, fever, constipation, or decreased appetite.

Manufactured by:
Gland Pharma Limited; Visakhapatnam,
Andhra Pradesh 530049 India

Manufactured for:
Hospira, Inc., Lake Forest, IL 60045 USA

LAB-0819-2.0

PRINCIPAL DISPLAY PANEL - 2.5 mg Vial Label

NDC 0409-1703-01

Bortezomib
for Injection

2.5 mg/vial

SINGLE-DOSE VIAL
DISCARD UNUSED PORTION

FOR INTRAVENOUS OR
SUBCUTANEOUS USE

Rx ONLY
CAUTION: Hazardous Agent
Hospira
CONTENTS: Lyophilized vial contains 2.5 mg
bortezomib and 25 mg mannitol.
Recommended Dosage: See Prescribing
Information.

PRINCIPAL DISPLAY PANEL - 2.5 mg Vial Carton

1 x 2.5 mg Single-dose Vial
NDC 0409-1703-01

Bortezomib
for Injection

2.5 mg/vial

SINGLE-DOSE VIAL
DISCARD UNUSED PORTION

FOR INTRAVENOUS OR
SUBCUTANEOUS USE

See Reconstitution
Information on Back

CAUTION: Hazardous Agent

Hospira

PRINCIPAL DISPLAY PANEL - 1 mg Vial Label

NDC 0409-1704-01

Bortezomib for Injection

1 mg/vial

SINGLE-DOSE VIAL
DISCARD UNUSED PORTION

FOR INTRAVENOUS OR SUBCUTANEOUS USE

Rx only
CAUTION: Hazardous Agent

Hospira

PRINCIPAL DISPLAY PANEL - 1 mg Vial Carton

1 x 1 mg Single-Dose Vial
NDC 0409-1704-01

Bortezomib
for Injection

1 mg/vial

SINGLE-DOSE VIAL
DISCARD UNUSED PORTION

FOR INTRAVENOUS OR
SUBCUTANEOUS USE

See Reconstitution
Information on Back

CAUTION: Hazardous Agent

Hospira